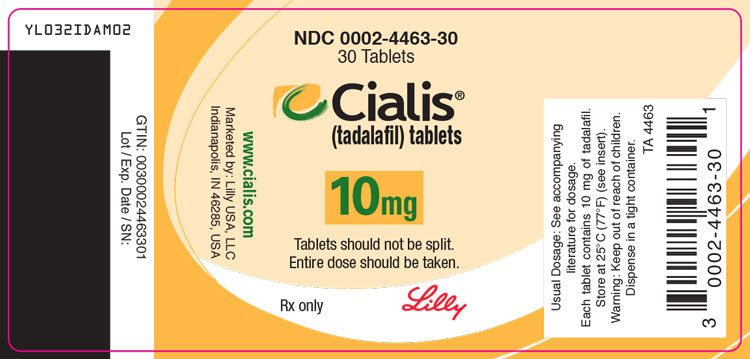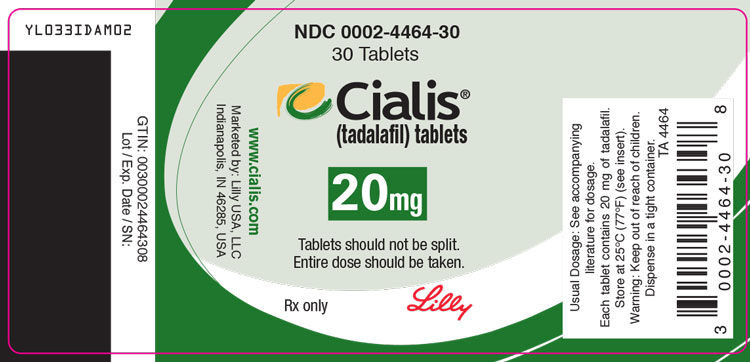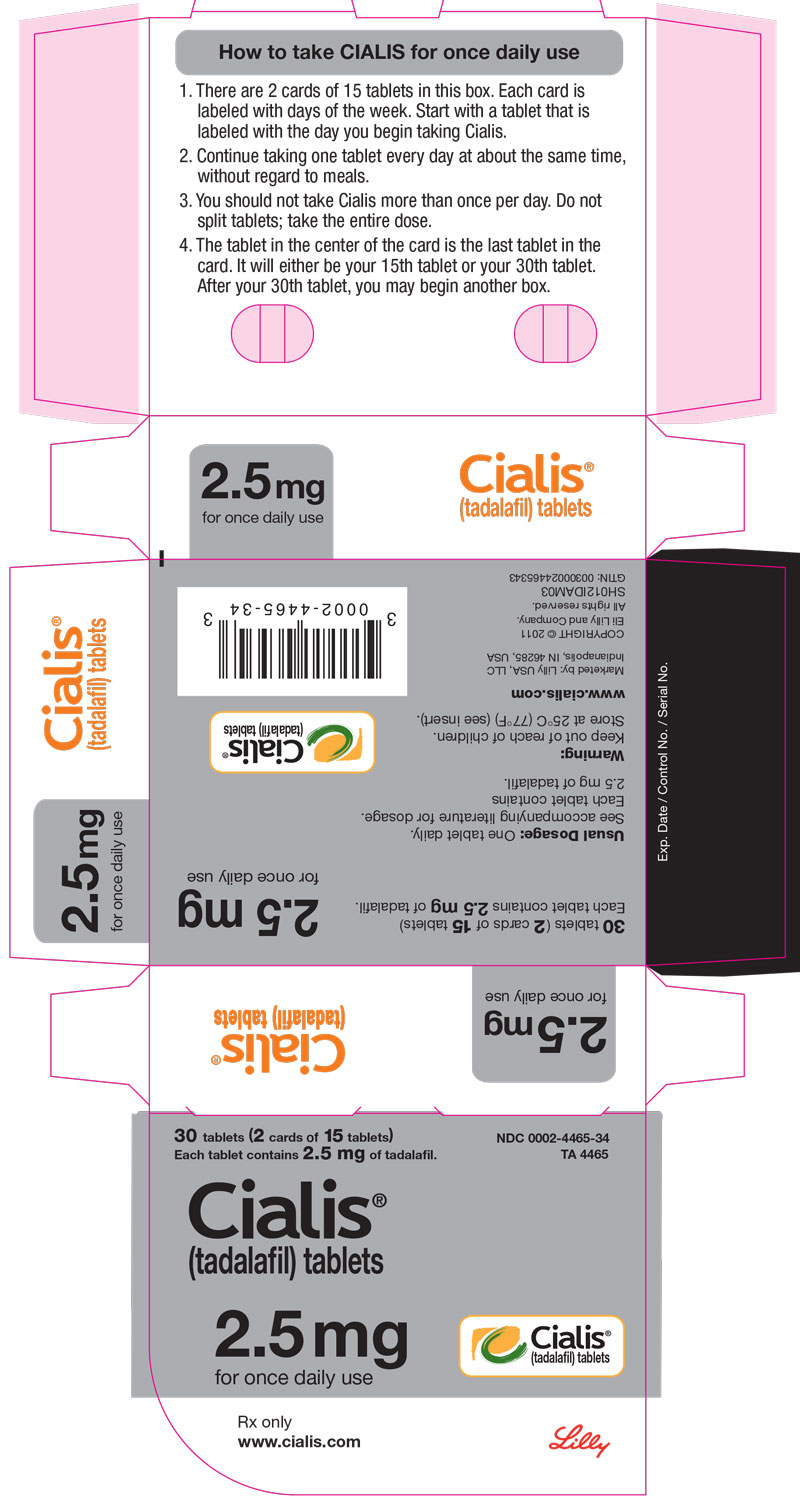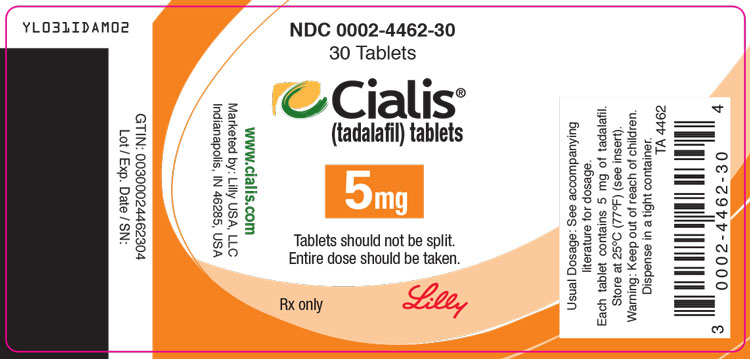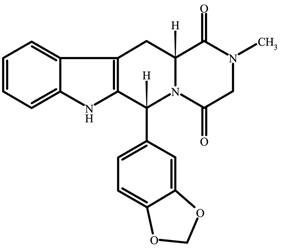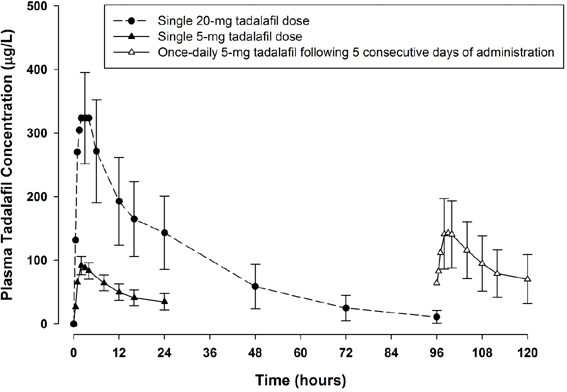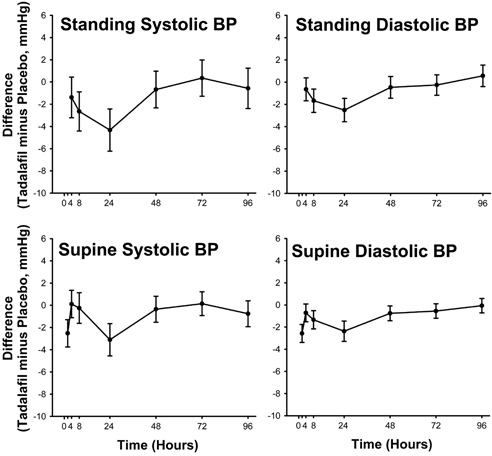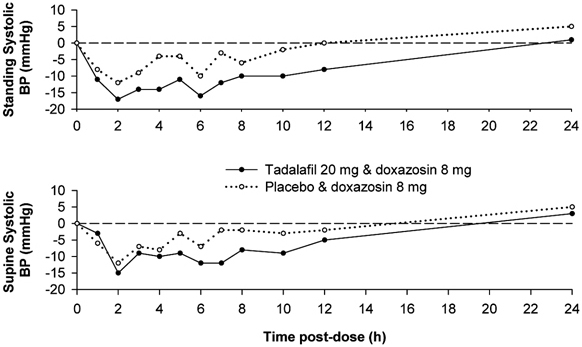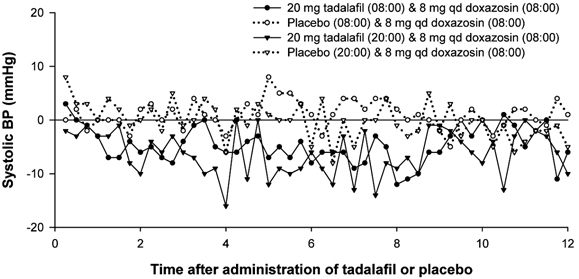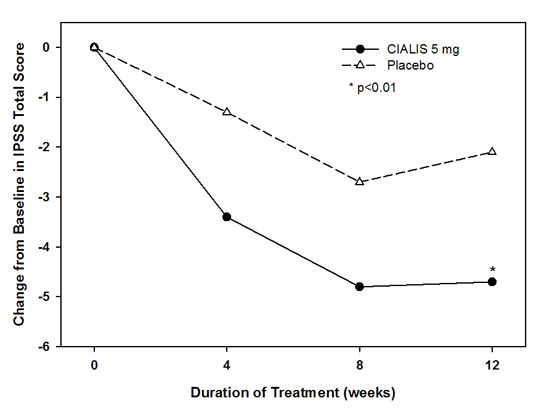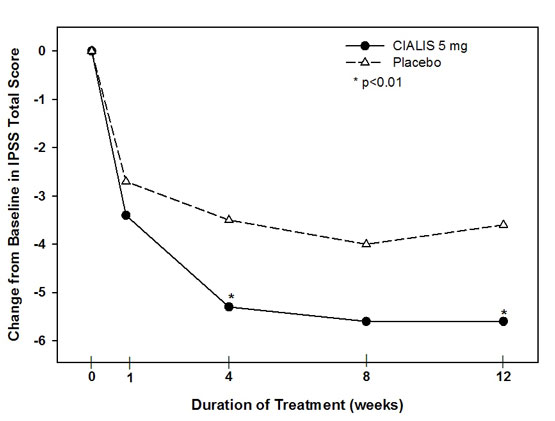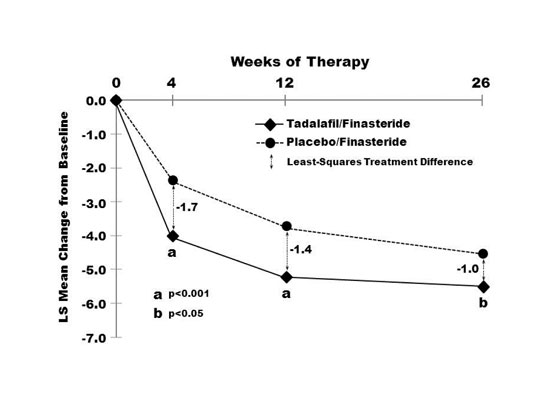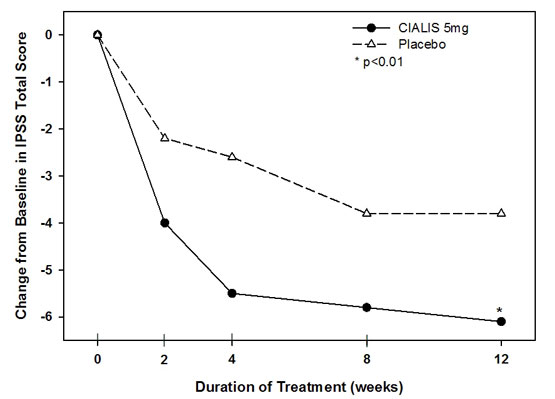 DRUG LABEL: Cialis
NDC: 0002-4465 | Form: TABLET, FILM COATED
Manufacturer: Eli Lilly and Company
Category: prescription | Type: HUMAN PRESCRIPTION DRUG LABEL
Date: 20251230

ACTIVE INGREDIENTS: Tadalafil 2.5 mg/1 1
INACTIVE INGREDIENTS: Hydroxypropyl cellulose, Unspecified; Hypromellose, Unspecified; Ferric Oxide Yellow; Ferric Oxide Red; Lactose monohydrate; Magnesium stearate; Microcrystalline cellulose; Sodium lauryl sulfate; Talc; Titanium dioxide; Croscarmellose sodium; Triacetin

HIGHLIGHTS OF PRESCRIBING INFORMATION

These highlights do not include all the information needed to use CIALIS safely and effectively. See full prescribing information for CIALIS.
CIALIS (tadalafil) tablets, for oral use
Initial U.S. Approval: 2003

1 INDICATIONS AND USAGE

CIALIS® is a phosphodiesterase 5 (PDE5) inhibitor indicated for the treatment of:

- erectile dysfunction (ED) (1.1)
- the signs and symptoms of benign prostatic hyperplasia (BPH) (1.2)
- ED and the signs and symptoms of BPH (ED/BPH) (1.3)

If CIALIS is used with finasteride to initiate BPH treatment, such use is recommended for up to 26 weeks (1.4).

2 DOSAGE AND ADMINISTRATION

- CIALIS for use as needed:
  - ED: Starting dose: 10 mg as needed prior to sexual activity. Increase to 20 mg or decrease to 5 mg based upon efficacy/tolerability. Improves erectile function compared to placebo up to 36 hours post dose. Not to be taken more than once per day (2.1).
- CIALIS for once daily use:
  - ED: 2.5 mg taken once daily, without regard to timing of sexual activity. May increase to 5 mg based upon efficacy and tolerability (2.2).
  - BPH: 5 mg, taken at approximately the same time every day (2.3)
  - ED and BPH: 5 mg, taken at approximately the same time every day (2.3, 2.4)
- CIALIS may be taken without regard to food (2.5).

3 DOSAGE FORMS AND STRENGTHS

Tablets: 2.5 mg, 5 mg, 10 mg, 20 mg (3).

4 CONTRAINDICATIONS

- Administration of CIALIS to patients using any form of organic nitrate is contraindicated. CIALIS was shown to potentiate the hypotensive effect of nitrates (4.1).
- History of known serious hypersensitivity reaction to CIALIS or ADCIRCA® (4.2).
- Administration with guanylate cyclase (GC) stimulators, such as riociguat (4.3).

5 WARNINGS AND PRECAUTIONS

- Patients should not use CIALIS if sex is inadvisable due to cardiovascular status (5.1).
- Use of CIALIS with alpha-blockers, antihypertensives or substantial amounts of alcohol (≥5 units) may lead to hypotension (5.6, 5.9).
- CIALIS is not recommended in combination with alpha-blockers for the treatment of BPH because efficacy of the combination has not been adequately studied and because of the risk of blood pressure lowering. Caution is advised when CIALIS is used as a treatment for ED in men taking alpha-blockers. (2.7, 5.6, 7.1, 12.2)
- Patients should seek emergency treatment if an erection lasts >4 hours. Use CIALIS with caution in patients predisposed to priapism (5.3).
- Patients should stop CIALIS and seek medical care if a sudden loss of vision occurs in one or both eyes, which could be a sign of non-arteritic anterior ischemic optic neuropathy (NAION). CIALIS should be used with caution, and only when the anticipated benefits outweigh the risks, in patients with a history of NAION. Patients with a "crowded" optic disc may also be at an increased risk of NAION (5.4, 6.2).
- Patients should stop CIALIS and seek prompt medical attention in the event of sudden decrease or loss of hearing (5.5).
- Prior to initiating treatment with CIALIS for BPH, consideration should be given to other urological conditions that may cause similar symptoms (5.14).

6 ADVERSE REACTIONS

Most common adverse reactions (≥2%) include headache, dyspepsia, back pain, myalgia, nasal congestion, flushing, and pain in limb (6.1).

To report SUSPECTED ADVERSE REACTIONS, contact Eli Lilly and Company at 1-800-LillyRx (1-800-545-5979) or FDA at 1-800-FDA-1088 or www.fda.gov/medwatch

7 DRUG INTERACTIONS

- CIALIS can potentiate the hypotensive effects of nitrates, alpha-blockers, antihypertensives or alcohol (7.1).
- CYP3A4 inhibitors (e.g. ketoconazole, ritonavir) increase CIALIS exposure (2.7, 5.10, 7.2) requiring dose adjustment:
  - CIALIS for use as needed: no more than 10 mg every 72 hours
  - CIALIS for once daily use: dose not to exceed 2.5 mg
- CYP3A4 inducers (e.g. rifampin) decrease CIALIS exposure (7.2).

8 USE IN SPECIFIC POPULATIONS

Hepatic Impairment (2.6, 5.8, 8.6):

- Mild or Moderate: Dosage adjustment may be needed.
- Severe: Use is not recommended.

Renal Impairment (2.6, 5.7, 8.7):

- Patients with creatinine clearance 30 to 50 mL/min: Dosage adjustment may be needed.
- Patients with creatinine clearance less than 30 mL/min or on hemodialysis: For use as needed: Dose should not exceed 5 mg every 72 hours. Once daily use is not recommended.

FULL PRESCRIBING INFORMATION

1 INDICATIONS AND USAGE

1.1 Erectile Dysfunction

CIALIS® is indicated for the treatment of erectile dysfunction (ED).

1.2 Benign Prostatic Hyperplasia

CIALIS is indicated for the treatment of the signs and symptoms of benign prostatic hyperplasia (BPH).

1.3 Erectile Dysfunction and Benign Prostatic Hyperplasia

CIALIS is indicated for the treatment of ED and the signs and symptoms of BPH (ED/BPH).

1.4 Limitation of Use

If CIALIS is used with finasteride to initiate BPH treatment, such use is recommended for up to 26 weeks because the incremental benefit of CIALIS decreases from 4 weeks until 26 weeks, and the incremental benefit of CIALIS beyond 26 weeks is unknown [see Clinical Studies (14.3)].

2 DOSAGE AND ADMINISTRATION

Do not split CIALIS tablets; entire dose should be taken.

2.1 CIALIS for Use as Needed for Erectile Dysfunction

- The recommended starting dose of CIALIS for use as needed in most patients is 10 mg, taken prior to anticipated sexual activity.
- The dose may be increased to 20 mg or decreased to 5 mg, based on individual efficacy and tolerability. The maximum recommended dosing frequency is once per day in most patients.
- CIALIS for use as needed was shown to improve erectile function compared to placebo up to 36 hours following dosing. Therefore, when advising patients on optimal use of CIALIS, this should be taken into consideration.

2.2 CIALIS for Once Daily Use for Erectile Dysfunction

- The recommended starting dose of CIALIS for once daily use is 2.5 mg, taken at approximately the same time every day, without regard to timing of sexual activity.
- The CIALIS dose for once daily use may be increased to 5 mg, based on individual efficacy and tolerability.

2.3 CIALIS for Once Daily Use for Benign Prostatic Hyperplasia

- The recommended dose of CIALIS for once daily use is 5 mg, taken at approximately the same time every day.
- When therapy for BPH is initiated with CIALIS and finasteride, the recommended dose of CIALIS for once daily use is 5 mg, taken at approximately the same time every day for up to 26 weeks.

2.4 CIALIS for Once Daily Use for Erectile Dysfunction and Benign Prostatic Hyperplasia

The recommended dose of CIALIS for once daily use is 5 mg, taken at approximately the same time every day, without regard to timing of sexual activity.

2.5 Use with Food

CIALIS may be taken without regard to food.

2.6 Use in Specific Populations

Renal Impairment

CIALIS for Use as Needed

- Creatinine clearance 30 to 50 mL/min: A starting dose of 5 mg not more than once per day is recommended, and the maximum dose is 10 mg not more than once in every 48 hours.
- Creatinine clearance less than 30 mL/min or on hemodialysis: The maximum dose is 5 mg not more than once in every 72 hours [see Warnings and Precautions (5.7) and Use in Specific Populations (8.7)].

CIALIS for Once Daily Use

Erectile Dysfunction

- Creatinine clearance less than 30 mL/min or on hemodialysis: CIALIS for once daily use is not recommended [see Warnings and Precautions (5.7) and Use in Specific Populations (8.7)].

Benign Prostatic Hyperplasia and Erectile Dysfunction/Benign Prostatic Hyperplasia

- Creatinine clearance 30 to 50 mL/min: A starting dose of 2.5 mg is recommended. An increase to 5 mg may be considered based on individual response.
- Creatinine clearance less than 30 mL/min or on hemodialysis: CIALIS for once daily use is not recommended [see Warnings and Precautions (5.7) and Use in Specific Populations (8.7)].

Hepatic Impairment

CIALIS for Use as Needed

- Mild or moderate (Child Pugh Class A or B): The dose should not exceed 10 mg once per day. The use of CIALIS once per day has not been extensively evaluated in patients with hepatic impairment and therefore, caution is advised.
- Severe (Child Pugh Class C): The use of CIALIS is not recommended [see Warnings and Precautions (5.8) and Use in Specific Populations (8.6)].

CIALIS for Once Daily Use

- Mild or moderate (Child Pugh Class A or B): CIALIS for once daily use has not been extensively evaluated in patients with hepatic impairment. Therefore, caution is advised if CIALIS for once daily use is prescribed to these patients.
- Severe (Child Pugh Class C): The use of CIALIS is not recommended [see Warnings and Precautions (5.8) and Use in Specific Populations (8.6)].

2.7 Concomitant Medications

Nitrates

Concomitant use of nitrates in any form is contraindicated [see Contraindications (4.1)].

Alpha-Blockers

ED — When CIALIS is coadministered with an alpha-blocker in patients being treated for ED, patients should be stable on alpha-blocker therapy prior to initiating treatment, and CIALIS should be initiated at the lowest recommended dose [see Warnings and Precautions (5.6), Drug Interactions (7.1), and Clinical Pharmacology (12.2)].

BPH — CIALIS is not recommended for use in combination with alpha-blockers for the treatment of BPH [see Warnings and Precautions (5.6), Drug Interactions (7.1), and Clinical Pharmacology (12.2)].

CYP3A4 Inhibitors

CIALIS for Use as Needed — For patients taking concomitant potent inhibitors of CYP3A4, such as ketoconazole or ritonavir, the maximum recommended dose of CIALIS is 10 mg, not to exceed once every 72 hours [see Warnings and Precautions (5.10) and Drug Interactions (7.2)].

CIALIS for Once Daily Use — For patients taking concomitant potent inhibitors of CYP3A4, such as ketoconazole or ritonavir, the maximum recommended dose is 2.5 mg [see Warnings and Precautions (5.10) and Drug Interactions (7.2)].

3 DOSAGE FORMS AND STRENGTHS

Four strengths of almond-shaped tablets are available in different sizes and different shades of yellow:

2.5 mg tablets debossed with “C 2 1/2”
5 mg tablets debossed with “C 5”
10 mg tablets debossed with “C 10”
20 mg tablets debossed with “C 20”

4 CONTRAINDICATIONS

4.1 Nitrates

Administration of CIALIS to patients who are using any form of organic nitrate, either regularly and/or intermittently, is contraindicated. In clinical pharmacology studies, CIALIS was shown to potentiate the hypotensive effect of nitrates [see Clinical Pharmacology (12.2)].

4.2 Hypersensitivity Reactions

CIALIS is contraindicated in patients with a known serious hypersensitivity to tadalafil (CIALIS or ADCIRCA®). Hypersensitivity reactions have been reported, including Stevens-Johnson syndrome and exfoliative dermatitis [see Adverse Reactions (6.2)].

4.3 Concomitant Guanylate Cyclase (GC) Stimulators

Do not use CIALIS in patients who are using a GC stimulator, such as riociguat. PDE5 inhibitors, including CIALIS, may potentiate the hypotensive effects of GC stimulators.

5 WARNINGS AND PRECAUTIONS

Evaluation of erectile dysfunction and BPH should include an appropriate medical assessment to identify potential underlying causes, as well as treatment options.

Before prescribing CIALIS, it is important to note the following:

5.1 Cardiovascular

Physicians should consider the cardiovascular status of their patients, since there is a degree of cardiac risk associated with sexual activity. Therefore, treatments for erectile dysfunction, including CIALIS, should not be used in men for whom sexual activity is inadvisable as a result of their underlying cardiovascular status. Patients who experience symptoms upon initiation of sexual activity should be advised to refrain from further sexual activity and seek immediate medical attention.

Physicians should discuss with patients the appropriate action in the event that they experience anginal chest pain requiring nitroglycerin following intake of CIALIS. In such a patient, who has taken CIALIS, where nitrate administration is deemed medically necessary for a life-threatening situation, at least 48 hours should have elapsed after the last dose of CIALIS before nitrate administration is considered. In such circumstances, nitrates should still only be administered under close medical supervision with appropriate hemodynamic monitoring. Therefore, patients who experience anginal chest pain after taking CIALIS should seek immediate medical attention. [see Contraindications (4.1) and Patient Counseling Information (17.1)].

Patients with left ventricular outflow obstruction, (e.g., aortic stenosis and idiopathic hypertrophic subaortic stenosis) can be sensitive to the action of vasodilators, including PDE5 inhibitors.

The following groups of patients with cardiovascular disease were not included in clinical safety and efficacy trials for CIALIS, and therefore until further information is available, CIALIS is not recommended for the following groups of patients:

- myocardial infarction within the last 90 days
- unstable angina or angina occurring during sexual intercourse
- New York Heart Association Class 2 or greater heart failure in the last 6 months
- uncontrolled arrhythmias, hypotension (<90/50 mm Hg), or uncontrolled hypertension
- stroke within the last 6 months.

As with other PDE5 inhibitors, tadalafil has mild systemic vasodilatory properties that may result in transient decreases in blood pressure. In a clinical pharmacology study, tadalafil 20 mg resulted in a mean maximal decrease in supine blood pressure, relative to placebo, of 1.6/0.8 mm Hg in healthy subjects [see Clinical Pharmacology (12.2)]. While this effect should not be of consequence in most patients, prior to prescribing CIALIS, physicians should carefully consider whether their patients with underlying cardiovascular disease could be affected adversely by such vasodilatory effects. Patients with severely impaired autonomic control of blood pressure may be particularly sensitive to the actions of vasodilators, including PDE5 inhibitors.

5.2 Potential for Drug Interactions When Taking CIALIS for Once Daily Use

Physicians should be aware that CIALIS for once daily use provides continuous plasma tadalafil levels and should consider this when evaluating the potential for interactions with medications (e.g., nitrates, alpha-blockers, anti-hypertensives and potent inhibitors of CYP3A4) and with substantial consumption of alcohol [see Drug Interactions (7.1, 7.2, 7.3)].

5.3 Prolonged Erection

There have been rare reports of prolonged erections greater than 4 hours and priapism (painful erections greater than 6 hours in duration) for this class of compounds. Priapism, if not treated promptly, can result in irreversible damage to the erectile tissue. Patients who have an erection lasting greater than 4 hours, whether painful or not, should seek emergency medical attention.

CIALIS should be used with caution in patients who have conditions that might predispose them to priapism (such as sickle cell anemia, multiple myeloma, or leukemia), or in patients with anatomical deformation of the penis (such as angulation, cavernosal fibrosis, or Peyronie's disease).

5.4 Effects on the Eye

Physicians should advise patients to stop use of all phosphodiesterase type 5 (PDE5) inhibitors, including CIALIS, and seek medical attention in the event of a sudden loss of vision in one or both eyes. Such an event may be a sign of non-arteritic anterior ischemic optic neuropathy (NAION), a rare condition and a cause of decreased vision, including permanent loss of vision, that has been reported rarely postmarketing in temporal association with the use of all PDE5 inhibitors. Based on published literature, the annual incidence of NAION is 2.5-11.8 cases per 100,000 in males aged ≥50.

An observational case-crossover study evaluated the risk of NAION when PDE5 inhibitor use, as a class, occurred immediately before NAION onset (within 5 half-lives), compared to PDE5 inhibitor use in a prior time period. The results suggest an approximate 2-fold increase in the risk of NAION, with a risk estimate of 2.15 (95% CI 1.06, 4.34). A similar study reported a consistent result, with a risk estimate of 2.27 (95% CI 0.99, 5.20). Other risk factors for NAION, such as the presence of "crowded" optic disc, may have contributed to the occurrence of NAION in these studies.

Neither the rare postmarketing reports, nor the association of PDE5 inhibitor use and NAION in the observational studies, substantiate a causal relationship between PDE5 inhibitor use and NAION [see Adverse Reactions (6.2)].

Physicians should consider whether their patients with underlying NAION risk factors could be adversely affected by use of PDE5 inhibitors. Individuals who have already experienced NAION are at increased risk of NAION recurrence. Therefore, PDE5 inhibitors, including CIALIS, should be used with caution in these patients and only when the anticipated benefits outweigh the risks. Individuals with "crowded" optic disc are also considered at greater risk for NAION compared to the general population; however, evidence is insufficient to support screening of prospective users of PDE5 inhibitors, including CIALIS, for this uncommon condition.

Patients with known hereditary degenerative retinal disorders, including retinitis pigmentosa, were not included in the clinical trials, and use in these patients is not recommended.

5.5 Sudden Hearing Loss

Physicians should advise patients to stop taking PDE5 inhibitors, including CIALIS, and seek prompt medical attention in the event of sudden decrease or loss of hearing. These events, which may be accompanied by tinnitus and dizziness, have been reported in temporal association to the intake of PDE5 inhibitors, including CIALIS. It is not possible to determine whether these events are related directly to the use of PDE5 inhibitors or to other factors [see Adverse Reactions (6.1, 6.2)].

5.6 Alpha-blockers and Antihypertensives

Physicians should discuss with patients the potential for CIALIS to augment the blood-pressure-lowering effect of alpha-blockers and antihypertensive medications [see Drug Interactions (7.1) and Clinical Pharmacology (12.2)].

Caution is advised when PDE5 inhibitors are coadministered with alpha-blockers. PDE5 inhibitors, including CIALIS, and alpha-adrenergic blocking agents are both vasodilators with blood-pressure-lowering effects. When vasodilators are used in combination, an additive effect on blood pressure may be anticipated. In some patients, concomitant use of these two drug classes can lower blood pressure significantly [see Drug Interactions (7.1) and Clinical Pharmacology (12.2)], which may lead to symptomatic hypotension (e.g., fainting). Consideration should be given to the following:

ED

- Patients should be stable on alpha-blocker therapy prior to initiating a PDE5 inhibitor. Patients who demonstrate hemodynamic instability on alpha-blocker therapy alone are at increased risk of symptomatic hypotension with concomitant use of PDE5 inhibitors.
- In those patients who are stable on alpha-blocker therapy, PDE5 inhibitors should be initiated at the lowest recommended dose.
- In those patients already taking an optimized dose of PDE5 inhibitor, alpha-blocker therapy should be initiated at the lowest dose. Stepwise increase in alpha-blocker dose may be associated with further lowering of blood pressure when taking a PDE5 inhibitor.
- Safety of combined use of PDE5 inhibitors and alpha-blockers may be affected by other variables, including intravascular volume depletion and other antihypertensive drugs.

[see Dosage and Administration (2.7) and Drug Interactions (7.1)].

BPH

- The efficacy of the coadministration of an alpha-blocker and CIALIS for the treatment of BPH has not been adequately studied, and due to the potential vasodilatory effects of combined use resulting in blood pressure lowering, the combination of CIALIS and alpha-blockers is not recommended for the treatment of BPH. [see Dosage and Administration (2.7), Drug Interactions (7.1), and Clinical Pharmacology (12.2.)].
- Patients on alpha-blocker therapy for BPH should discontinue their alpha-blocker at least one day prior to starting CIALIS for once daily use for the treatment of BPH.

5.7 Renal Impairment

CIALIS for Use as Needed

CIALIS should be limited to 5 mg not more than once in every 72 hours in patients with creatinine clearance less than 30 mL/min or end-stage renal disease on hemodialysis. The starting dose of CIALIS in patients with creatinine clearance 30 – 50 mL/min should be 5 mg not more than once per day, and the maximum dose should be limited to 10 mg not more than once in every 48 hours. [see Use in Specific Populations (8.7)].

CIALIS for Once Daily Use

ED

Due to increased tadalafil exposure (AUC), limited clinical experience, and the lack of ability to influence clearance by dialysis, CIALIS for once daily use is not recommended in patients with creatinine clearance less than 30 mL/min [see Use in Specific Populations (8.7)].

BPH and ED/BPH

Due to increased tadalafil exposure (AUC), limited clinical experience, and the lack of ability to influence clearance by dialysis, CIALIS for once daily use is not recommended in patients with creatinine clearance less than 30 mL/min. In patients with creatinine clearance 30 – 50 mL/min, start dosing at 2.5 mg once daily, and increase the dose to 5 mg once daily based upon individual response [see Dosage and Administration (2.6), Use in Specific Populations (8.7), and Clinical Pharmacology (12.3)].

5.8 Hepatic Impairment

CIALIS for Use as Needed

In patients with mild or moderate hepatic impairment, the dose of CIALIS should not exceed 10 mg. Because of insufficient information in patients with severe hepatic impairment, use of CIALIS in this group is not recommended [see Use in Specific Populations (8.6)].

CIALIS for Once Daily Use

CIALIS for once daily use has not been extensively evaluated in patients with mild or moderate hepatic impairment. Therefore, caution is advised if CIALIS for once daily use is prescribed to these patients. Because of insufficient information in patients with severe hepatic impairment, use of CIALIS in this group is not recommended [see Use in Specific Populations (8.6)].

5.9 Alcohol

Patients should be made aware that both alcohol and CIALIS, a PDE5 inhibitor, act as mild vasodilators. When mild vasodilators are taken in combination, blood-pressure-lowering effects of each individual compound may be increased. Therefore, physicians should inform patients that substantial consumption of alcohol (e.g., 5 units or greater) in combination with CIALIS can increase the potential for orthostatic signs and symptoms, including increase in heart rate, decrease in standing blood pressure, dizziness, and headache [see Clinical Pharmacology (12.2)].

5.10 Concomitant Use of Potent Inhibitors of Cytochrome P450 3A4 (CYP3A4)

CIALIS is metabolized predominantly by CYP3A4 in the liver. The dose of CIALIS for use as needed should be limited to 10 mg no more than once every 72 hours in patients taking potent inhibitors of CYP3A4 such as ritonavir, ketoconazole, and itraconazole [see Drug Interactions (7.2)]. In patients taking potent inhibitors of CYP3A4 and CIALIS for once daily use, the maximum recommended dose is 2.5 mg [see Dosage and Administration (2.7)].

5.11 Combination With Other PDE5 Inhibitors or Erectile Dysfunction Therapies

The safety and efficacy of combinations of CIALIS and other PDE5 inhibitors or treatments for erectile dysfunction have not been studied. Inform patients not to take CIALIS with other PDE5 inhibitors, including ADCIRCA.

5.12 Effects on Bleeding

Studies in vitro have demonstrated that tadalafil is a selective inhibitor of PDE5. PDE5 is found in platelets. When administered in combination with aspirin, tadalafil 20 mg did not prolong bleeding time, relative to aspirin alone. CIALIS has not been administered to patients with bleeding disorders or significant active peptic ulceration. Although CIALIS has not been shown to increase bleeding times in healthy subjects, use in patients with bleeding disorders or significant active peptic ulceration should be based upon a careful risk-benefit assessment and caution.

5.13 Counseling Patients About Sexually Transmitted Diseases

The use of CIALIS offers no protection against sexually transmitted diseases. Counseling patients about the protective measures necessary to guard against sexually transmitted diseases, including Human Immunodeficiency Virus (HIV) should be considered.

5.14 Consideration of Other Urological Conditions Prior to Initiating Treatment for BPH

Prior to initiating treatment with CIALIS for BPH, consideration should be given to other urological conditions that may cause similar symptoms. In addition, prostate cancer and BPH may coexist.

6 ADVERSE REACTIONS

6.1 Clinical Trials Experience

Because clinical trials are conducted under widely varying conditions, adverse reaction rates observed in the clinical trials of a drug cannot be directly compared to rates in the clinical trials of another drug and may not reflect the rates observed in practice.

Tadalafil was administered to over 9000 men during clinical trials worldwide. In trials of CIALIS for once daily use, a total of 1434, 905, and 115 were treated for at least 6 months, 1 year, and 2 years, respectively. For CIALIS for use as needed, over 1300 and 1000 subjects were treated for at least 6 months and 1 year, respectively.

CIALIS for Use as Needed for ED

In eight primary placebo-controlled clinical studies of 12 weeks duration, mean age was 59 years (range 22 to 88) and the discontinuation rate due to adverse events in patients treated with tadalafil 10 or 20 mg was 3.1%, compared to 1.4% in placebo treated patients.

When taken as recommended in the placebo-controlled clinical trials, the following adverse reactions were reported (see Table 1) for CIALIS for use as needed:

Table 1: Treatment-Emergent Adverse Reactions Reported by ≥2% of Patients Treated with CIALIS (10 or 20 mg) and More Frequent on Drug than Placebo in the Eight Primary Placebo-Controlled Clinical Studies (Including a Study in Patients with Diabetes) for CIALIS for Use as Needed for ED
Adverse Reaction | Placebo (N=476) | Tadalafil 5 mg (N=151) | Tadalafil 10 mg (N=394) | Tadalafil 20 mg (N=635)
Headache | 5% | 11% | 11% | 15%
Dyspepsia | 1% | 4% | 8% | 10%
Back pain | 3% | 3% | 5% | 6%
Myalgia | 1% | 1% | 4% | 3%
Nasal congestion | 1% | 2% | 3% | 3%
Flushinga | 1% | 2% | 3% | 3%
Pain in limb | 1% | 1% | 3% | 3%
a The term flushing includes: facial flushing and flushing

CIALIS for Once Daily Use for ED

In three placebo-controlled clinical trials of 12 or 24 weeks duration, mean age was 58 years (range 21 to 82) and the discontinuation rate due to adverse events in patients treated with tadalafil was 4.1%, compared to 2.8% in placebo-treated patients.

The following adverse reactions were reported (see Table 2) in clinical trials of 12 weeks duration:

Table 2: Treatment-Emergent Adverse Reactions Reported by ≥2% of Patients Treated with CIALIS for Once Daily Use (2.5 or 5 mg) and More Frequent on Drug than Placebo in the Three Primary Placebo-Controlled Phase 3 Studies of 12 weeks Treatment Duration (Including a Study in Patients with Diabetes) for CIALIS for Once Daily Use for ED
Adverse Reaction | Placebo (N=248) | Tadalafil 2.5 mg (N=196) | Tadalafil 5 mg (N=304)
Headache | 5% | 3% | 6%
Dyspepsia | 2% | 4% | 5%
Nasopharyngitis | 4% | 4% | 3%
Back pain | 1% | 3% | 3%
Upper respiratory tract infection | 1% | 3% | 3%
Flushing | 1% | 1% | 3%
Myalgia | 1% | 2% | 2%
Cough | 0% | 4% | 2%
Diarrhea | 0% | 1% | 2%
Nasal congestion | 0% | 2% | 2%
Pain in extremity | 0% | 1% | 2%
Urinary tract infection | 0% | 2% | 0%
Gastroesophageal reflux disease | 0% | 2% | 1%
Abdominal pain | 0% | 2% | 1%

The following adverse reactions were reported (see Table 3) over 24 weeks treatment duration in one placebo-controlled clinical study:

Table 3: Treatment-Emergent Adverse Reactions Reported by ≥2% of Patients Treated with CIALIS for Once Daily Use (2.5 or 5 mg) and More Frequent on Drug than Placebo in One Placebo-Controlled Clinical Study of 24 Weeks Treatment Duration for CIALIS for Once Daily Use for ED
Adverse Reaction | Placebo (N=94) | Tadalafil 2.5 mg (N=96) | Tadalafil 5 mg (N=97)
Nasopharyngitis | 5% | 6% | 6%
Gastroenteritis | 2% | 3% | 5%
Back pain | 3% | 5% | 2%
Upper respiratory tract infection | 0% | 3% | 4%
Dyspepsia | 1% | 4% | 1%
Gastroesophageal reflux disease | 0% | 3% | 2%
Myalgia | 2% | 4% | 1%
Hypertension | 0% | 1% | 3%
Nasal congestion | 0% | 0% | 4%

CIALIS for Once Daily Use for BPH and for ED and BPH

In three placebo-controlled clinical trials of 12 weeks duration, two in patients with BPH and one in patients with ED and BPH, the mean age was 63 years (range 44 to 93) and the discontinuation rate due to adverse events in patients treated with tadalafil was 3.6% compared to 1.6% in placebo-treated patients. Adverse reactions leading to discontinuation reported by at least 2 patients treated with tadalafil included headache, upper abdominal pain, and myalgia. The following adverse reactions were reported (see Table 4).

Table 4: Treatment-Emergent Adverse Reactions Reported by ≥1% of Patients Treated with CIALIS for Once Daily Use (5 mg) and More Frequent on Drug than Placebo in Three Placebo-Controlled Clinical Studies of 12 Weeks Treatment Duration, including Two Studies for CIALIS for Once Daily Use for BPH and One Study for ED and BPH
Adverse Reaction | Placebo (N=576) | Tadalafil 5 mg (N=581)
Headache | 2.3% | 4.1%
Dyspepsia | 0.2% | 2.4%
Back pain | 1.4% | 2.4%
Nasopharyngitis | 1.6% | 2.1%
Diarrhea | 1.0% | 1.4%
Pain in extremity | 0.0% | 1.4%
Myalgia | 0.3% | 1.2%
Dizziness | 0.5% | 1.0%

Additional, less frequent adverse reactions (<1%) reported in the controlled clinical trials of CIALIS for BPH or ED and BPH included: gastroesophageal reflux disease, upper abdominal pain, nausea, vomiting, arthralgia, and muscle spasm.

Back pain or myalgia was reported at incidence rates described in Tables 1 through 4. In tadalafil clinical pharmacology trials, back pain or myalgia generally occurred 12 to 24 hours after dosing and typically resolved within 48 hours. The back pain/myalgia associated with tadalafil treatment was characterized by diffuse bilateral lower lumbar, gluteal, thigh, or thoracolumbar muscular discomfort and was exacerbated by recumbency. In general, pain was reported as mild or moderate in severity and resolved without medical treatment, but severe back pain was reported with a low frequency (<5% of all reports). When medical treatment was necessary, acetaminophen or non-steroidal anti-inflammatory drugs were generally effective; however, in a small percentage of subjects who required treatment, a mild narcotic (e.g., codeine) was used. Overall, approximately 0.5% of all subjects treated with CIALIS for on demand use discontinued treatment as a consequence of back pain/myalgia. In the 1-year open label extension study, back pain and myalgia were reported in 5.5% and 1.3% of patients, respectively. Diagnostic testing, including measures for inflammation, muscle injury, or renal damage revealed no evidence of medically significant underlying pathology. Incidence rates for CIALIS for once daily use for ED, BPH and BPH/ED are described in Tables 2, 3 and 4. In studies of CIALIS for once daily use, adverse reactions of back pain and myalgia were generally mild or moderate with a discontinuation rate of <1% across all indications.

Across placebo-controlled studies with CIALIS for use as needed for ED, diarrhea was reported more frequently in patients 65 years of age and older who were treated with CIALIS (2.5% of patients) [see Use in Specific Populations (8.5)].

Across all studies with any CIALIS dose, reports of changes in color vision were rare (<0.1% of patients).

The following section identifies additional, less frequent events (<2%) reported in controlled clinical trials of CIALIS for once daily use or use as needed. A causal relationship of these events to CIALIS is uncertain. Excluded from this list are those events that were minor, those with no plausible relation to drug use, and reports too imprecise to be meaningful:

Body as a Whole — asthenia, face edema, fatigue, pain, peripheral edema

Cardiovascular — angina pectoris, chest pain, hypotension, myocardial infarction, postural hypotension, palpitations, syncope, tachycardia

Digestive — abnormal liver function tests, dry mouth, dysphagia, esophagitis, gastritis, GGTP increased, loose stools, nausea, upper abdominal pain, vomiting, gastroesophageal reflux disease, hemorrhoidal hemorrhage, rectal hemorrhage

Musculoskeletal — arthralgia, neck pain

Nervous — dizziness, hypesthesia, insomnia, paresthesia, somnolence, vertigo

Renal and Urinary — renal impairment

Respiratory — dyspnea, epistaxis, pharyngitis

Skin and Appendages — pruritus, rash, sweating

Ophthalmologic — blurred vision, changes in color vision, conjunctivitis (including conjunctival hyperemia), eye pain, lacrimation increase, swelling of eyelids

Otologic — sudden decrease or loss of hearing, tinnitus

Urogenital — erection increased, spontaneous penile erection

6.2 Postmarketing Experience

The following adverse reactions have been identified during post approval use of CIALIS. Because these reactions are reported voluntarily from a population of uncertain size, it is not always possible to reliably estimate their frequency or establish a causal relationship to drug exposure. These events have been chosen for inclusion either due to their seriousness, reporting frequency, lack of clear alternative causation, or a combination of these factors.

Cardiovascular and Cerebrovascular — Serious cardiovascular events, including myocardial infarction, sudden cardiac death, stroke, chest pain, palpitations, and tachycardia, have been reported postmarketing in temporal association with the use of tadalafil. Most, but not all, of these patients had preexisting cardiovascular risk factors. Many of these events were reported to occur during or shortly after sexual activity, and a few were reported to occur shortly after the use of CIALIS without sexual activity. Others were reported to have occurred hours to days after the use of CIALIS and sexual activity. It is not possible to determine whether these events are related directly to CIALIS, to sexual activity, to the patient's underlying cardiovascular disease, to a combination of these factors, or to other factors [see Warnings and Precautions (5.1)].

Body as a Whole — hypersensitivity reactions including urticaria, Stevens-Johnson syndrome, and exfoliative dermatitis

Nervous — migraine, seizure and seizure recurrence, transient global amnesia

Ophthalmologic — visual field defect, retinal vein occlusion, retinal artery occlusion

Non-arteritic anterior ischemic optic neuropathy (NAION), a cause of decreased vision including permanent loss of vision, has been reported rarely postmarketing in temporal association with the use of PDE5 inhibitors, including CIALIS. Most, but not all, of these patients had underlying anatomic or vascular risk factors for development of NAION, including but not necessarily limited to: low cup to disc ratio ("crowded disc"), age over 50, diabetes, hypertension, coronary artery disease, hyperlipidemia, and smoking [see Warnings and Precautions (5.4)].

Otologic — Cases of sudden decrease or loss of hearing have been reported postmarketing in temporal association with the use of PDE5 inhibitors, including CIALIS. In some of the cases, medical conditions and other factors were reported that may have also played a role in the otologic adverse events. In many cases, medical follow-up information was limited. It is not possible to determine whether these reported events are related directly to the use of CIALIS, to the patient's underlying risk factors for hearing loss, a combination of these factors, or to other factors [see Warnings and Precautions (5.5)].

Urogenital — priapism [see Warnings and Precautions (5.3)].

7 DRUG INTERACTIONS

7.1 Potential for Pharmacodynamic Interactions with CIALIS

Nitrates — Administration of CIALIS to patients who are using any form of organic nitrate, is contraindicated. In clinical pharmacology studies, CIALIS was shown to potentiate the hypotensive effect of nitrates. In a patient who has taken CIALIS, where nitrate administration is deemed medically necessary in a life-threatening situation, at least 48 hours should elapse after the last dose of CIALIS before nitrate administration is considered. In such circumstances, nitrates should still only be administered under close medical supervision with appropriate hemodynamic monitoring [see Dosage and Administration (2.7), Contraindications (4.1), and Clinical Pharmacology (12.2)].

Alpha-Blockers — Caution is advised when PDE5 inhibitors are coadministered with alpha-blockers. PDE5 inhibitors, including CIALIS, and alpha-adrenergic blocking agents are both vasodilators with blood-pressure-lowering effects. When vasodilators are used in combination, an additive effect on blood pressure may be anticipated. Clinical pharmacology studies have been conducted with coadministration of tadalafil with doxazosin, tamsulosin or alfuzosin. [see Dosage and Administration (2.7), Warnings and Precautions (5.6), and Clinical Pharmacology (12.2)].

Antihypertensives — PDE5 inhibitors, including tadalafil, are mild systemic vasodilators. Clinical pharmacology studies were conducted to assess the effect of tadalafil on the potentiation of the blood-pressure-lowering effects of selected antihypertensive medications (amlodipine, angiotensin II receptor blockers, bendrofluazide, enalapril, and metoprolol). Small reductions in blood pressure occurred following coadministration of tadalafil with these agents compared with placebo. [see Warnings and Precautions (5.6) and Clinical Pharmacology (12.2)].

Alcohol — Both alcohol and tadalafil, a PDE5 inhibitor, act as mild vasodilators. When mild vasodilators are taken in combination, blood-pressure-lowering effects of each individual compound may be increased. Substantial consumption of alcohol (e.g., 5 units or greater) in combination with CIALIS can increase the potential for orthostatic signs and symptoms, including increase in heart rate, decrease in standing blood pressure, dizziness, and headache. Tadalafil did not affect alcohol plasma concentrations and alcohol did not affect tadalafil plasma concentrations. [see Warnings and Precautions (5.9) and Clinical Pharmacology (12.2)].

7.2 Potential for Other Drugs to Affect CIALIS

[See Dosage and Administration (2.7) and Warnings and Precautions (5.10)].

Antacids — Simultaneous administration of an antacid (magnesium hydroxide/aluminum hydroxide) and tadalafil reduced the apparent rate of absorption of tadalafil without altering exposure (AUC) to tadalafil.

H2 Antagonists (e.g. Nizatidine) — An increase in gastric pH resulting from administration of nizatidine had no significant effect on pharmacokinetics.

Cytochrome P450 Inhibitors — CIALIS is a substrate of and predominantly metabolized by CYP3A4. Studies have shown that drugs that inhibit CYP3A4 can increase tadalafil exposure.

CYP3A4 (e.g., Ketoconazole) — Ketoconazole (400 mg daily), a selective and potent inhibitor of CYP3A4, increased tadalafil 20 mg single-dose exposure (AUC) by 312% and Cmax by 22%, relative to the values for tadalafil 20 mg alone. Ketoconazole (200 mg daily) increased tadalafil 10-mg single-dose exposure (AUC) by 107% and Cmax by 15%, relative to the values for tadalafil 10 mg alone [see Dosage and Administration (2.7)].

Although specific interactions have not been studied, other CYP3A4 inhibitors, such as erythromycin, itraconazole, and grapefruit juice, would likely increase tadalafil exposure.

HIV Protease inhibitor — Ritonavir (500 mg or 600 mg twice daily at steady state), an inhibitor of CYP3A4, CYP2C9, CYP2C19, and CYP2D6, increased tadalafil 20-mg single-dose exposure (AUC) by 32% with a 30% reduction in Cmax, relative to the values for tadalafil 20 mg alone. Ritonavir (200 mg twice daily), increased tadalafil 20-mg single-dose exposure (AUC) by 124% with no change in Cmax, relative to the values for tadalafil 20 mg alone. Although specific interactions have not been studied, other HIV protease inhibitors would likely increase tadalafil exposure [see Dosage and Administration (2.7)].

Cytochrome P450 Inducers — Studies have shown that drugs that induce CYP3A4 can decrease tadalafil exposure.

CYP3A4 (e.g., Rifampin) — Rifampin (600 mg daily), a CYP3A4 inducer, reduced tadalafil 10-mg single-dose exposure (AUC) by 88% and Cmax by 46%, relative to the values for tadalafil 10 mg alone. Although specific interactions have not been studied, other CYP3A4 inducers, such as carbamazepine, phenytoin, and phenobarbital, would likely decrease tadalafil exposure. No dose adjustment is warranted. The reduced exposure of tadalafil with the coadministration of rifampin or other CYP3A4 inducers can be anticipated to decrease the efficacy of CIALIS for once daily use; the magnitude of decreased efficacy is unknown.

7.3 Potential for CIALIS to Affect Other Drugs

Aspirin — Tadalafil did not potentiate the increase in bleeding time caused by aspirin.

Cytochrome P450 Substrates — CIALIS is not expected to cause clinically significant inhibition or induction of the clearance of drugs metabolized by cytochrome P450 (CYP) isoforms. Studies have shown that tadalafil does not inhibit or induce P450 isoforms CYP1A2, CYP3A4, CYP2C9, CYP2C19, CYP2D6, and CYP2E1.

CYP1A2 (e.g. Theophylline) — Tadalafil had no significant effect on the pharmacokinetics of theophylline. When tadalafil was administered to subjects taking theophylline, a small augmentation (3 beats per minute) of the increase in heart rate associated with theophylline was observed.

CYP2C9 (e.g. Warfarin) — Tadalafil had no significant effect on exposure (AUC) to S-warfarin or R-warfarin, nor did tadalafil affect changes in prothrombin time induced by warfarin.

CYP3A4 (e.g. Midazolam or Lovastatin) — Tadalafil had no significant effect on exposure (AUC) to midazolam or lovastatin.

P-glycoprotein (e.g. Digoxin) — Coadministration of tadalafil (40 mg once per day) for 10 days did not have a significant effect on the steady-state pharmacokinetics of digoxin (0.25 mg/day) in healthy subjects.

8 USE IN SPECIFIC POPULATIONS

8.1 Pregnancy

Risk Summary

CIALIS (tadalafil) is not indicated for use in females.

There are no data with the use of CIALIS in pregnant women to inform any drug-associated risks for adverse developmental outcomes. In animal reproduction studies, no adverse developmental effects were observed with oral administration of tadalafil to pregnant rats or mice during organogenesis at exposures up to 11 times the maximum recommended human dose (MRHD) of 20 mg/day (see Data).

Data

Animal Data

Animal reproduction studies showed no evidence of teratogenicity, embryotoxicity, or fetotoxicity when tadalafil was given orally to pregnant rats or mice at exposures up to 11 times the maximum recommended human dose (MRHD) of 20 mg/day during organogenesis. In a prenatal/postnatal developmental study in rats, postnatal pup survival decreased following maternal exposure to tadalafil doses greater than 10 times the MRHD based on AUC. Signs of maternal toxicity occurred at doses greater than 16 times the MRHD based on AUC. Surviving offspring had normal development and reproductive performance.

In another rat prenatal and postnatal development study at doses of 60, 200, and 1000 mg/kg, a reduction in postnatal survival of pups was observed. The no observed effect level (NOEL) for maternal toxicity was 200 mg/kg/day and for developmental toxicity was 30 mg/kg/day. This gives approximately 16 and 10 fold exposure multiples, respectively, of the human AUC for the MRHD of 20 mg.

Tadalafil and/or its metabolites cross the placenta, resulting in fetal exposure in rats.

8.2 Lactation

Risk Summary

CIALIS is not indicated for use in females.

There is no information on the presence of tadalafil and/or metabolites in human milk, the effects on the breastfed child, or the effects on milk production. Tadalafil and/or its metabolites are present in the milk of lactating rats at concentrations approximately 2.4-fold greater than found in the plasma.

8.3 Females and Males of Reproductive Potential

Infertility

Based on the data from 3 studies in adult males, tadalafil decreased sperm concentrations in the study of 10 mg tadalafil for 6 months and the study of 20 mg tadalafil for 9 months. This effect was not seen in the study of 20 mg tadalafil taken for 6 months. There was no adverse effect of tadalafil 10 mg or 20 mg on mean concentrations of testosterone, luteinizing hormone or follicle stimulating hormone. The clinical significance of the decreased sperm concentrations in the two studies is unknown. There have been no studies evaluating the effect of tadalafil on fertility in men [see Clinical Pharmacology (12.2)].

Based on studies in animals, a decrease in spermatogenesis was observed in dogs, but not in rats [see Nonclinical Toxicology (13.1)].

8.4 Pediatric Use

CIALIS is not indicated for use in pediatric patients. Safety and efficacy in patients below the age of 18 years have not been established.

A randomized, double-blind, placebo-controlled trial in pediatric patients (7 to 14 years of age) with Duchenne muscular dystrophy, who received CIALIS 0.3 mg/kg, CIALIS 0.6 mg/kg, or placebo daily for 48 weeks failed to demonstrate any benefit of treatment with CIALIS on a range of assessments of muscle strength and performance.

Juvenile Animal Study

No adverse effects were observed in a study in which tadalafil was administered orally at doses of 60, 200, and 1000 mg/kg/day to juvenile rats on postnatal days 14 to 90. The highest plasma tadalafil exposures (AUC) achieved were approximately 10-fold that observed at the MRHD.

8.5 Geriatric Use

Of the total number of subjects in ED clinical studies of tadalafil, approximately 19 percent were 65 and over, while approximately 2 percent were 75 and over. Of the total number of subjects in BPH clinical studies of tadalafil (including the ED/BPH study), approximately 40 percent were over 65, while approximately 10 percent were 75 and over. In these clinical trials, no overall differences in efficacy or safety were observed between older (>65 and ≥75 years of age) and younger subjects (≤65 years of age). However, in placebo-controlled studies with CIALIS for use as needed for ED, diarrhea was reported more frequently in patients 65 years of age and older who were treated with CIALIS (2.5% of patients) [see Adverse Reactions (6.1)]. No dose adjustment is warranted based on age alone. However, a greater sensitivity to medications in some older individuals should be considered. [see Clinical Pharmacology (12.3)].

8.6 Hepatic Impairment

In clinical pharmacology studies, tadalafil exposure (AUC) in subjects with mild or moderate hepatic impairment (Child-Pugh Class A or B) was comparable to exposure in healthy subjects when a dose of 10 mg was administered. There are no available data for doses higher than 10 mg of tadalafil in patients with hepatic impairment. Insufficient data are available for subjects with severe hepatic impairment (Child-Pugh Class C). [see Dosage and Administration (2.6) and Warnings and Precautions (5.8)].

8.7 Renal Impairment

In clinical pharmacology studies using single-dose tadalafil (5 to 10 mg), tadalafil exposure (AUC) doubled in subjects with creatinine clearance 30 to 80 mL/min. In subjects with end-stage renal disease on hemodialysis, there was a two-fold increase in Cmax and 2.7- to 4.8-fold increase in AUC following single-dose administration of 10 or 20 mg tadalafil. Exposure to total methylcatechol (unconjugated plus glucuronide) was 2- to 4-fold higher in subjects with renal impairment, compared to those with normal renal function. Hemodialysis (performed between 24 and 30 hours post-dose) contributed negligibly to tadalafil or metabolite elimination. In a clinical pharmacology study (N=28) at a dose of 10 mg, back pain was reported as a limiting adverse event in male patients with creatinine clearance 30 to 50 mL/min. At a dose of 5 mg, the incidence and severity of back pain was not significantly different than in the general population. In patients on hemodialysis taking 10- or 20-mg tadalafil, there were no reported cases of back pain. [see Dosage and Administration (2.6) and Warnings and Precautions (5.7)].

10 OVERDOSAGE

Single doses up to 500 mg have been given to healthy subjects, and multiple daily doses up to 100 mg have been given to patients. Adverse events were similar to those seen at lower doses. In cases of overdose, standard supportive measures should be adopted as required. Hemodialysis contributes negligibly to tadalafil elimination.

11 DESCRIPTION

CIALIS (tadalafil) is a selective inhibitor of cyclic guanosine monophosphate (cGMP)-specific phosphodiesterase type 5 (PDE5). Tadalafil has the empirical formula C22H19N3O4 representing a molecular weight of 389.41. The structural formula is:

The chemical designation is pyrazino[1´,2´:1,6]pyrido[3,4-b]indole-1,4-dione, 6-(1,3-benzodioxol-5-yl)-2,3,6,7,12,12a-hexahydro-2-methyl-, (6R,12aR)-. It is a crystalline solid that is practically insoluble in water and very slightly soluble in ethanol.

CIALIS is available as almond-shaped tablets for oral administration. Each tablet contains 2.5, 5, 10, or 20 mg of tadalafil and the following inactive ingredients: croscarmellose sodium, hydroxypropyl cellulose, hypromellose, iron oxide, lactose monohydrate, magnesium stearate, microcrystalline cellulose, sodium lauryl sulfate, talc, titanium dioxide, and triacetin.

12 CLINICAL PHARMACOLOGY

12.1 Mechanism of Action

Penile erection during sexual stimulation is caused by increased penile blood flow resulting from the relaxation of penile arteries and corpus cavernosal smooth muscle. This response is mediated by the release of nitric oxide (NO) from nerve terminals and endothelial cells, which stimulates the synthesis of cGMP in smooth muscle cells. Cyclic GMP causes smooth muscle relaxation and increased blood flow into the corpus cavernosum. The inhibition of phosphodiesterase type 5 (PDE5) enhances erectile function by increasing the amount of cGMP. Tadalafil inhibits PDE5. Because sexual stimulation is required to initiate the local release of nitric oxide, the inhibition of PDE5 by tadalafil has no effect in the absence of sexual stimulation.

The effect of PDE5 inhibition on cGMP concentration in the corpus cavernosum and pulmonary arteries is also observed in the smooth muscle of the prostate, the bladder and their vascular supply. The mechanism for reducing BPH symptoms has not been established.

Studies in vitro have demonstrated that tadalafil is a selective inhibitor of PDE5. PDE5 is found in the smooth muscle of the corpus cavernosum, prostate, and bladder as well as in vascular and visceral smooth muscle, skeletal muscle, urethra, platelets, kidney, lung, cerebellum, heart, liver, testis, seminal vesicle, and pancreas.

In vitro studies have shown that the effect of tadalafil is more potent on PDE5 than on other phosphodiesterases. These studies have shown that tadalafil is >10,000-fold more potent for PDE5 than for PDE1, PDE2, PDE4, and PDE7 enzymes, which are found in the heart, brain, blood vessels, liver, leukocytes, skeletal muscle, and other organs. Tadalafil is >10,000-fold more potent for PDE5 than for PDE3, an enzyme found in the heart and blood vessels. Additionally, tadalafil is 700-fold more potent for PDE5 than for PDE6, which is found in the retina and is responsible for phototransduction. Tadalafil is >9,000-fold more potent for PDE5 than for PDE8, PDE9, and PDE10. Tadalafil is 14-fold more potent for PDE5 than for PDE11A1 and 40-fold more potent for PDE5 than for PDE11A4, two of the four known forms of PDE11. PDE11 is an enzyme found in human prostate, testes, skeletal muscle and in other tissues (e.g., adrenal cortex). In vitro, tadalafil inhibits human recombinant PDE11A1 and, to a lesser degree, PDE11A4 activities at concentrations within the therapeutic range. The physiological role and clinical consequence of PDE11 inhibition in humans have not been defined.

12.2 Pharmacodynamics

Effects on Blood Pressure

Tadalafil 20 mg administered to healthy male subjects produced no significant difference compared to placebo in supine systolic and diastolic blood pressure (difference in the mean maximal decrease of 1.6/0.8 mm Hg, respectively) and in standing systolic and diastolic blood pressure (difference in the mean maximal decrease of 0.2/4.6 mm Hg, respectively). In addition, there was no significant effect on heart rate.

Effects on Blood Pressure When Administered with Nitrates

In clinical pharmacology studies, tadalafil (5 to 20 mg) was shown to potentiate the hypotensive effect of nitrates. Therefore, the use of CIALIS in patients taking any form of nitrates is contraindicated [see Contraindications (4.1)].

A study was conducted to assess the degree of interaction between nitroglycerin and tadalafil, should nitroglycerin be required in an emergency situation after tadalafil was taken. This was a double-blind, placebo-controlled, crossover study in 150 male subjects at least 40 years of age (including subjects with diabetes mellitus and/or controlled hypertension) and receiving daily doses of tadalafil 20 mg or matching placebo for 7 days. Subjects were administered a single dose of 0.4 mg sublingual nitroglycerin (NTG) at pre-specified timepoints, following their last dose of tadalafil (2, 4, 8, 24, 48, 72, and 96 hours after tadalafil). The objective of the study was to determine when, after tadalafil dosing, no apparent blood pressure interaction was observed. In this study, a significant interaction between tadalafil and NTG was observed at each timepoint up to and including 24 hours. At 48 hours, by most hemodynamic measures, the interaction between tadalafil and NTG was not observed, although a few more tadalafil subjects compared to placebo experienced greater blood-pressure lowering at this timepoint. After 48 hours, the interaction was not detectable (see Figure 1).

Figure 1: Mean Maximal Change in Blood Pressure (Tadalafil Minus Placebo, Point Estimate with 90% CI) in Response to Sublingual Nitroglycerin at 2 (Supine Only), 4, 8, 24, 48, 72, and 96 Hours after the Last Dose of Tadalafil 20 mg or Placebo

Therefore, CIALIS administration with nitrates is contraindicated. In a patient who has taken CIALIS, where nitrate administration is deemed medically necessary in a life-threatening situation, at least 48 hours should elapse after the last dose of CIALIS before nitrate administration is considered. In such circumstances, nitrates should still only be administered under close medical supervision with appropriate hemodynamic monitoring [see Contraindications (4.1)].

Effect on Blood Pressure When Administered With Alpha-Blockers

Six randomized, double-blinded, crossover clinical pharmacology studies were conducted to investigate the potential interaction of tadalafil with alpha-blocker agents in healthy male subjects [see Dosage and Administration (2.7) and Warnings and Precautions (5.6)]. In four studies, a single oral dose of tadalafil was administered to healthy male subjects taking daily (at least 7 days duration) an oral alpha-blocker. In two studies, a daily oral alpha-blocker (at least 7 days duration) was administered to healthy male subjects taking repeated daily doses of tadalafil.

Doxazosin — Three clinical pharmacology studies were conducted with tadalafil and doxazosin, an alpha[1]-adrenergic blocker.

In the first doxazosin study, a single oral dose of tadalafil 20 mg or placebo was administered in a 2-period, crossover design to healthy subjects taking oral doxazosin 8 mg daily (N=18 subjects). Doxazosin was administered at the same time as tadalafil or placebo after a minimum of seven days of doxazosin dosing (see Table 5 and Figure 2).

Table 5: Doxazosin (8 mg/day) Study 1: Mean Maximal Decrease (95% CI) in Systolic Blood Pressure
Placebo-subtracted mean maximal decrease in systolic blood pressure (mm Hg) | Tadalafil 20 mg
Supine | 3.6 (-1.5, 8.8)
Standing | 9.8 (4.1, 15.5)

Figure 2: Doxazosin Study 1: Mean Change from Baseline in Systolic Blood Pressure

Blood pressure was measured manually at 1, 2, 3, 4, 5, 6, 7, 8, 10, 12, and 24 hours after tadalafil or placebo administration. Outliers were defined as subjects with a standing systolic blood pressure of <85 mm Hg or a decrease from baseline in standing systolic blood pressure of >30 mm Hg at one or more time points. There were nine and three outliers following administration of tadalafil 20 mg and placebo, respectively. Five and two subjects were outliers due to a decrease from baseline in standing systolic BP of >30 mm Hg, while five and one subject were outliers due to standing systolic BP <85 mm Hg following tadalafil and placebo, respectively. Severe adverse events potentially related to blood-pressure effects were assessed. No such events were reported following placebo. Two such events were reported following administration of tadalafil. Vertigo was reported in one subject that began 7 hours after dosing and lasted about 5 days. This subject previously experienced a mild episode of vertigo on doxazosin and placebo. Dizziness was reported in another subject that began 25 minutes after dosing and lasted 1 day. No syncope was reported.

In the second doxazosin study, a single oral dose of tadalafil 20 mg was administered to healthy subjects taking oral doxazosin, either 4 or 8 mg daily. The study (N=72 subjects) was conducted in three parts, each a 3-period crossover.

In part A (N=24), subjects were titrated to doxazosin 4 mg administered daily at 8 a.m. Tadalafil was administered at either 8 a.m., 4 p.m., or 8 p.m. There was no placebo control.

In part B (N=24), subjects were titrated to doxazosin 4 mg administered daily at 8 p.m. Tadalafil was administered at either 8 a.m., 4 p.m., or 8 p.m. There was no placebo control.

In part C (N=24), subjects were titrated to doxazosin 8 mg administered daily at 8 a.m. In this part, tadalafil or placebo were administered at either 8 a.m. or 8 p.m.

The placebo-subtracted mean maximal decreases in systolic blood pressure over a 12-hour period after dosing in the placebo-controlled portion of the study (part C) are shown in Table 6 and Figure 3.

Table 6: Doxazosin (8 mg/day) Study 2 (Part C): Mean Maximal Decrease in Systolic Blood Pressure
Placebo-subtracted mean maximal decrease in systolic blood pressure (mm Hg) | Tadalafil 20 mg at 8 a.m. | Tadalafil 20 mg at 8 p.m.
Ambulatory Blood-Pressure Monitoring (ABPM) | 7 | 8

Figure 3: Doxazosin Study 2 (Part C): Mean Change from Time-Matched Baseline in Systolic Blood Pressure

Blood pressure was measured by ABPM every 15 to 30 minutes for up to 36 hours after tadalafil or placebo. Subjects were categorized as outliers if one or more systolic blood pressure readings of <85 mm Hg were recorded or one or more decreases in systolic blood pressure of >30 mm Hg from a time-matched baseline occurred during the analysis interval.

Of the 24 subjects in part C, 16 subjects were categorized as outliers following administration of tadalafil and 6 subjects were categorized as outliers following placebo during the 24-hour period after 8 a.m. dosing of tadalafil or placebo. Of these, 5 and 2 were outliers due to systolic BP <85 mm Hg, while 15 and 4 were outliers due to a decrease from baseline in systolic BP of >30 mm Hg following tadalafil and placebo, respectively.

During the 24-hour period after 8 p.m. dosing, 17 subjects were categorized as outliers following administration of tadalafil and 7 subjects following placebo. Of these, 10 and 2 subjects were outliers due to systolic BP <85 mm Hg, while 15 and 5 subjects were outliers due to a decrease from baseline in systolic BP of >30 mm Hg, following tadalafil and placebo, respectively.

Some additional subjects in both the tadalafil and placebo groups were categorized as outliers in the period beyond 24 hours.

Severe adverse events potentially related to blood-pressure effects were assessed. In the study (N=72 subjects), 2 such events were reported following administration of tadalafil (symptomatic hypotension in one subject that began 10 hours after dosing and lasted approximately 1 hour, and dizziness in another subject that began 11 hours after dosing and lasted 2 minutes). No such events were reported following placebo. In the period prior to tadalafil dosing, one severe event (dizziness) was reported in a subject during the doxazosin run-in phase.

In the third doxazosin study, healthy subjects (N=45 treated; 37 completed) received 28 days of once per day dosing of tadalafil 5 mg or placebo in a two-period crossover design. After 7 days, doxazosin was initiated at 1 mg and titrated up to 4 mg daily over the last 21 days of each period (7 days on 1 mg; 7 days of 2 mg; 7 days of 4 mg doxazosin). The results are shown in Table 7.

Table 7: Doxazosin Study 3: Mean Maximal Decrease (95% CI) in Systolic Blood Pressure
Placebo-subtracted mean maximal decrease in systolic blood pressure |  | Tadalafil 5 mg
Day 1 of 4 mg Doxazosin | Supine | 2.4 (-0.4, 5.2)
Day 1 of 4 mg Doxazosin | Standing | -0.5 (-4.0, 3.1)
Day 7 of 4 mg Doxazosin | Supine | 2.8 (-0.1, 5.7)
Day 7 of 4 mg Doxazosin | Standing | 1.1 (-2.9, 5.0)

Blood pressure was measured manually pre-dose at two time points (-30 and -15 minutes) and then at 1, 2, 3, 4, 5, 6, 7, 8, 10, 12 and 24 hours post dose on the first day of each doxazosin dose, (1 mg, 2 mg, 4 mg), as well as on the seventh day of 4 mg doxazosin administration.

Following the first dose of doxazosin 1 mg, there were no outliers on tadalafil 5 mg and one outlier on placebo due to a decrease from baseline in standing systolic BP of >30 mm Hg.

There were 2 outliers on tadalafil 5 mg and none on placebo following the first dose of doxazosin 2 mg due to a decrease from baseline in standing systolic BP of >30 mm Hg.

There were no outliers on tadalafil 5 mg and two on placebo following the first dose of doxazosin 4 mg due to a decrease from baseline in standing systolic BP of >30 mm Hg. There was one outlier on tadalafil 5 mg and three on placebo following the first dose of doxazosin 4 mg due to standing systolic BP <85 mm Hg. Following the seventh day of doxazosin 4 mg, there were no outliers on tadalafil 5 mg, one subject on placebo had a decrease >30 mm Hg in standing systolic blood pressure, and one subject on placebo had standing systolic blood pressure <85 mm Hg. All adverse events potentially related to blood pressure effects were rated as mild or moderate. There were two episodes of syncope in this study, one subject following a dose of tadalafil 5 mg alone, and another subject following coadministration of tadalafil 5 mg and doxazosin 4 mg.

Tamsulosin — In the first tamsulosin study, a single oral dose of tadalafil 10, 20 mg, or placebo was administered in a 3 period, crossover design to healthy subjects taking 0.4 mg once per day tamsulosin, a selective alpha[1A]-adrenergic blocker (N=18 subjects). Tadalafil or placebo was administered 2 hours after tamsulosin following a minimum of seven days of tamsulosin dosing.

Table 8: Tamsulosin (0.4 mg/day) Study 1: Mean Maximal Decrease (95% CI) in Systolic Blood Pressure
Placebo-subtracted mean maximal decrease in systolic blood pressure (mm Hg) | Tadalafil 10 mg | Tadalafil 20 mg
Supine | 3.2 (-2.3, 8.6) | 3.2 (-2.3, 8.7)
Standing | 1.7 (-4.7, 8.1) | 2.3 (-4.1, 8.7)

Blood pressure was measured manually at 1, 2, 3, 4, 5, 6, 7, 8, 10, 12, and 24 hours after tadalafil or placebo dosing. There were 2, 2, and 1 outliers (subjects with a decrease from baseline in standing systolic blood pressure of >30 mm Hg at one or more time points) following administration of tadalafil 10 mg, 20 mg, and placebo, respectively. There were no subjects with a standing systolic blood pressure <85 mm Hg. No severe adverse events potentially related to blood-pressure effects were reported. No syncope was reported.

In the second tamsulosin study, healthy subjects (N=39 treated; and 35 completed) received 14 days of once per day dosing of tadalafil 5 mg or placebo in a two-period crossover design. Daily dosing of tamsulosin 0.4 mg was added for the last seven days of each period.

Table 9: Tamsulosin Study 2: Mean Maximal Decrease (95% CI) in Systolic Blood Pressure
Placebo-subtracted mean maximal decrease in systolic blood pressure |  | Tadalafil 5 mg
Day 1 of 0.4 mg Tamsulosin | Supine | -0.1 (-2.2, 1.9)
Day 1 of 0.4 mg Tamsulosin | Standing | 0.9 (-1.4, 3.2)
Day 7 of 0.4 mg Tamsulosin | Supine | 1.2 (-1.2, 3.6)
Day 7 of 0.4 mg Tamsulosin | Standing | 1.2 (-1.0, 3.5)

Blood pressure was measured manually pre-dose at two time points (-30 and -15 minutes) and then at 1, 2, 3, 4, 5, 6, 7, 8, 10, 12, and 24 hours post dose on the first, sixth and seventh days of tamsulosin administration. There were no outliers (subjects with a decrease from baseline in standing systolic blood pressure of >30 mm Hg at one or more time points). One subject on placebo plus tamsulosin (Day 7) and one subject on tadalafil plus tamsulosin (Day 6) had standing systolic blood pressure <85 mm Hg. No severe adverse events potentially related to blood pressure were reported. No syncope was reported.

Alfuzosin — A single oral dose of tadalafil 20 mg or placebo was administered in a 2-period, crossover design to healthy subjects taking once-daily alfuzosin HCl 10 mg extended-release tablets, an alpha[1]-adrenergic blocker (N=17 completed subjects). Tadalafil or placebo was administered 4 hours after alfuzosin following a minimum of seven days of alfuzosin dosing.

Table 10: Alfuzosin (10 mg/day) Study: Mean Maximal Decrease (95% CI) in Systolic Blood Pressure
Placebo-subtracted mean maximal decrease in systolic blood pressure (mm Hg) | Tadalafil 20 mg
Supine | 2.2 (-0.9,-5.2)
Standing | 4.4 (-0.2, 8.9)

Blood pressure was measured manually at 1, 2, 3, 4, 6, 8, 10, 20, and 24 hours after tadalafil or placebo dosing. There was 1 outlier (subject with a standing systolic blood pressure <85 mm Hg) following administration of tadalafil 20 mg. There were no subjects with a decrease from baseline in standing systolic blood pressure of >30 mm Hg at one or more time points. No severe adverse events potentially related to blood pressure effects were reported. No syncope was reported.

Effects on Blood Pressure When Administered with Antihypertensives

Amlodipine — A study was conducted to assess the interaction of amlodipine (5 mg daily) and tadalafil 10 mg. There was no effect of tadalafil on amlodipine blood levels and no effect of amlodipine on tadalafil blood levels. The mean reduction in supine systolic/diastolic blood pressure due to tadalafil 10 mg in subjects taking amlodipine was 3/2 mm Hg, compared to placebo. In a similar study using tadalafil 20 mg, there were no clinically significant differences between tadalafil and placebo in subjects taking amlodipine.

Angiotensin II receptor blockers (with and without other antihypertensives) — A study was conducted to assess the interaction of angiotensin II receptor blockers and tadalafil 20 mg. Subjects in the study were taking any marketed angiotensin II receptor blocker, either alone, as a component of a combination product, or as part of a multiple antihypertensive regimen. Following dosing, ambulatory measurements of blood pressure revealed differences between tadalafil and placebo of 8/4 mm Hg in systolic/diastolic blood pressure.

Bendrofluazide — A study was conducted to assess the interaction of bendrofluazide (2.5 mg daily) and tadalafil 10 mg. Following dosing, the mean reduction in supine systolic/diastolic blood pressure due to tadalafil 10 mg in subjects taking bendrofluazide was 6/4 mm Hg, compared to placebo.

Enalapril — A study was conducted to assess the interaction of enalapril (10 to 20 mg daily) and tadalafil 10 mg. Following dosing, the mean reduction in supine systolic/diastolic blood pressure due to tadalafil 10 mg in subjects taking enalapril was 4/1 mm Hg, compared to placebo.

Metoprolol — A study was conducted to assess the interaction of sustained-release metoprolol (25 to 200 mg daily) and tadalafil 10 mg. Following dosing, the mean reduction in supine systolic/diastolic blood pressure due to tadalafil 10 mg in subjects taking metoprolol was 5/3 mm Hg, compared to placebo.

Effects on Blood Pressure When Administered with Alcohol

Alcohol and PDE5 inhibitors, including tadalafil, are mild systemic vasodilators. The interaction of tadalafil with alcohol was evaluated in 3 clinical pharmacology studies. In 2 of these, alcohol was administered at a dose of 0.7 g/kg, which is equivalent to approximately 6 ounces of 80-proof vodka in an 80-kg male, and tadalafil was administered at a dose of 10 mg in one study and 20 mg in another. In both these studies, all patients imbibed the entire alcohol dose within 10 minutes of starting. In one of these two studies, blood alcohol levels of 0.08% were confirmed. In these two studies, more patients had clinically significant decreases in blood pressure on the combination of tadalafil and alcohol as compared to alcohol alone. Some subjects reported postural dizziness, and orthostatic hypotension was observed in some subjects. When tadalafil 20 mg was administered with a lower dose of alcohol (0.6 g/kg, which is equivalent to approximately 4 ounces of 80-proof vodka, administered in less than 10 minutes), orthostatic hypotension was not observed, dizziness occurred with similar frequency to alcohol alone, and the hypotensive effects of alcohol were not potentiated.

Tadalafil did not affect alcohol plasma concentrations and alcohol did not affect tadalafil plasma concentrations.

Effects on Exercise Stress Testing

The effects of tadalafil on cardiac function, hemodynamics, and exercise tolerance were investigated in a single clinical pharmacology study. In this blinded crossover trial, 23 subjects with stable coronary artery disease and evidence of exercise-induced cardiac ischemia were enrolled. The primary endpoint was time to cardiac ischemia. The mean difference in total exercise time was 3 seconds (tadalafil 10 mg minus placebo), which represented no clinically meaningful difference. Further statistical analysis demonstrated that tadalafil was non-inferior to placebo with respect to time to ischemia. Of note, in this study, in some subjects who received tadalafil followed by sublingual nitroglycerin in the post-exercise period, clinically significant reductions in blood pressure were observed, consistent with the augmentation by tadalafil of the blood-pressure-lowering effects of nitrates.

Effects on Vision

Single oral doses of phosphodiesterase inhibitors have demonstrated transient dose-related impairment of color discrimination (blue/green), using the Farnsworth-Munsell 100-hue test, with peak effects near the time of peak plasma levels. This finding is consistent with the inhibition of PDE6, which is involved in phototransduction in the retina. In a study to assess the effects of a single dose of tadalafil 40 mg on vision (N=59), no effects were observed on visual acuity, intraocular pressure, or pupilometry. Across all clinical studies with CIALIS, reports of changes in color vision were rare (<0.1% of patients).

Effects on Sperm Characteristics

Three studies were conducted in men to assess the potential effect on sperm characteristics of tadalafil 10 mg (one 6 month study) and 20 mg (one 6 month and one 9 month study) administered daily. There were no adverse effects on sperm morphology or sperm motility in any of the three studies. In the study of 10 mg tadalafil for 6 months and the study of 20 mg tadalafil for 9 months, results showed a decrease in mean sperm concentrations relative to placebo, although these differences were not clinically meaningful. This effect was not seen in the study of 20 mg tadalafil taken for 6 months. In addition there was no adverse effect on mean concentrations of reproductive hormones, testosterone, luteinizing hormone or follicle stimulating hormone with either 10 or 20 mg of tadalafil compared to placebo.

Effects on Cardiac Electrophysiology

The effect of a single 100-mg dose of tadalafil on the QT interval was evaluated at the time of peak tadalafil concentration in a randomized, double-blinded, placebo, and active (intravenous ibutilide) -controlled crossover study in 90 healthy males aged 18 to 53 years. The mean change in QTc (Fridericia QT correction) for tadalafil, relative to placebo, was 3.5 milliseconds (two-sided 90% CI=1.9, 5.1). The mean change in QTc (Individual QT correction) for tadalafil, relative to placebo, was 2.8 milliseconds (two-sided 90% CI=1.2, 4.4). A 100-mg dose of tadalafil (5 times the highest recommended dose) was chosen because this dose yields exposures covering those observed upon coadministration of tadalafil with potent CYP3A4 inhibitors or those observed in renal impairment. In this study, the mean increase in heart rate associated with a 100-mg dose of tadalafil compared to placebo was 3.1 beats per minute.

12.3 Pharmacokinetics

Over a dose range of 2.5 to 20 mg, tadalafil exposure (AUC) increases proportionally with dose in healthy subjects. Steady-state plasma concentrations are attained within 5 days of once per day dosing and exposure is approximately 1.6-fold greater than after a single dose. Mean tadalafil concentrations measured after the administration of a single oral dose of 20 mg and single and once daily multiple doses of 5 mg, from a separate study, (see Figure 4) to healthy male subjects are depicted in Figure 4.

Figure 4: Plasma tadalafil concentrations (mean ± SD) following a single 20-mg tadalafil dose and single and once daily multiple doses of 5 mg

Absorption — After single oral-dose administration, the maximum observed plasma concentration (Cmax) of tadalafil is achieved between 30 minutes and 6 hours (median time of 2 hours). Absolute bioavailability of tadalafil following oral dosing has not been determined.

The rate and extent of absorption of tadalafil are not influenced by food; thus CIALIS may be taken with or without food.

Distribution — The mean apparent volume of distribution following oral administration is approximately 63 L, indicating that tadalafil is distributed into tissues. At therapeutic concentrations, 94% of tadalafil in plasma is bound to proteins.

Less than 0.0005% of the administered dose appeared in the semen of healthy subjects.

Metabolism — Tadalafil is predominantly metabolized by CYP3A4 to a catechol metabolite. The catechol metabolite undergoes extensive methylation and glucuronidation to form the methylcatechol and methylcatechol glucuronide conjugate, respectively. The major circulating metabolite is the methylcatechol glucuronide. Methylcatechol concentrations are less than 10% of glucuronide concentrations. In vitro data suggests that metabolites are not expected to be pharmacologically active at observed metabolite concentrations.

Excretion — The mean oral clearance for tadalafil is 2.5 L/hr and the mean terminal half-life is 17.5 hours in healthy subjects. Tadalafil is excreted predominantly as metabolites, mainly in the feces (approximately 61% of the dose) and to a lesser extent in the urine (approximately 36% of the dose).

Geriatric — Healthy male elderly subjects (65 years or over) had a lower oral clearance of tadalafil, resulting in 25% higher exposure (AUC) with no effect on Cmax relative to that observed in healthy subjects 19 to 45 years of age. No dose adjustment is warranted based on age alone. However, greater sensitivity to medications in some older individuals should be considered [see Use in Specific Populations (8.5)].

Patients with Diabetes Mellitus — In male patients with diabetes mellitus after a 10 mg tadalafil dose, exposure (AUC) was reduced approximately 19% and Cmax was 5% lower than that observed in healthy subjects. No dose adjustment is warranted.

Patients with BPH — In patients with BPH following single and multiple-doses of 20 mg tadalafil, no statistically significant differences in exposure (AUC and Cmax) were observed between elderly (70 to 85 years) and younger (≤60 years of age) subjects. No dose adjustment is warranted.

13 NONCLINICAL TOXICOLOGY

13.1 Carcinogenesis, Mutagenesis, Impairment of Fertility

Carcinogenesis — Tadalafil was not carcinogenic to rats or mice when administered daily for 2 years at doses up to 400 mg/kg/day. Systemic drug exposures, as measured by AUC of unbound tadalafil, were approximately 10-fold for mice, and 14- and 26-fold for male and female rats, respectively, the exposures in human males given Maximum Recommended Human Dose (MRHD) of 20 mg.

Mutagenesis — Tadalafil was not mutagenic in the in vitro bacterial Ames assays or the forward mutation test in mouse lymphoma cells. Tadalafil was not clastogenic in the in vitro chromosomal aberration test in human lymphocytes or the in vivo rat micronucleus assays.

Impairment of Fertility — There were no effects on fertility, reproductive performance or reproductive organ morphology in male or female rats given oral doses of tadalafil up to 400 mg/kg/day, a dose producing AUCs for unbound tadalafil of 14-fold for males or 26-fold for females the exposures observed in human males given the MRHD of 20 mg. In beagle dogs given tadalafil daily for 3 to 12 months, there was treatment-related non-reversible degeneration and atrophy of the seminiferous tubular epithelium in the testes in 20-100% of the dogs that resulted in a decrease in spermatogenesis in 40-75% of the dogs at doses of ≥10 mg/kg/day. Systemic exposure (based on AUC) at no-observed-adverse-effect-level (NOAEL) (10 mg/kg/day) for unbound tadalafil was similar to that expected in humans at the MRHD of 20 mg.

There were no treatment-related testicular findings in rats or mice treated with doses up to 400 mg/kg/day for 2 years.

13.2 Animal Toxicology and/or Pharmacology

Animal studies showed vascular inflammation in tadalafil-treated mice, rats, and dogs. In mice and rats, lymphoid necrosis and hemorrhage were seen in the spleen, thymus, and mesenteric lymph nodes at unbound tadalafil exposure of 2- to 33-fold above the human exposure (AUCs) at the MRHD of 20 mg. In dogs, an increased incidence of disseminated arteritis was observed in 1- and 6-month studies at unbound tadalafil exposure of 1- to 54-fold above the human exposure (AUC) at the MRHD of 20 mg. In a 12-month dog study, no disseminated arteritis was observed, but 2 dogs exhibited marked decreases in white blood cells (neutrophils) and moderate decreases in platelets with inflammatory signs at unbound tadalafil exposures of approximately 14- to 18-fold the human exposure at the MRHD of 20 mg. The abnormal blood-cell findings were reversible within 2 weeks after stopping treatment.

14 CLINICAL STUDIES

14.1 CIALIS for Use as Needed for ED

The efficacy and safety of tadalafil in the treatment of erectile dysfunction has been evaluated in 22 clinical trials of up to 24-weeks duration, involving over 4000 patients. CIALIS, when taken as needed up to once per day, was shown to be effective in improving erectile function in men with erectile dysfunction (ED).

CIALIS was studied in the general ED population in 7 randomized, multicenter, double-blinded, placebo-controlled, parallel-arm design, primary efficacy and safety studies of 12-weeks duration. Two of these studies were conducted in the United States and 5 were conducted in centers outside the US. Additional efficacy and safety studies were performed in ED patients with diabetes mellitus and in patients who developed ED status post bilateral nerve-sparing radical prostatectomy.

In these 7 trials, CIALIS was taken as needed, at doses ranging from 2.5 to 20 mg, up to once per day. Patients were free to choose the time interval between dose administration and the time of sexual attempts. Food and alcohol intake were not restricted.

Several assessment tools were used to evaluate the effect of CIALIS on erectile function. The 3 primary outcome measures were the Erectile Function (EF) domain of the International Index of Erectile Function (IIEF) and Questions 2 and 3 from Sexual Encounter Profile (SEP). The IIEF is a 4-week recall questionnaire that was administered at the end of a treatment-free baseline period and subsequently at follow-up visits after randomization. The IIEF EF domain has a 30-point total score, where higher scores reflect better erectile function. SEP is a diary in which patients recorded each sexual attempt made throughout the study. SEP Question 2 asks, “Were you able to insert your penis into the partner's vagina?” SEP Question 3 asks, “Did your erection last long enough for you to have successful intercourse?” The overall percentage of successful attempts to insert the penis into the vagina (SEP2) and to maintain the erection for successful intercourse (SEP3) is derived for each patient.

Results in ED Population in US Trials — The 2 primary US efficacy and safety trials included a total of 402 men with erectile dysfunction, with a mean age of 59 years (range 27 to 87 years). The population was 78% White, 14% Black, 7% Hispanic, and 1% of other ethnicities, and included patients with ED of various severities, etiologies (organic, psychogenic, mixed), and with multiple co-morbid conditions, including diabetes mellitus, hypertension, and other cardiovascular disease. Most (>90%) patients reported ED of at least 1-year duration. Study A was conducted primarily in academic centers. Study B was conducted primarily in community-based urology practices. In each of these 2 trials, CIALIS 20 mg showed clinically meaningful and statistically significant improvements in all 3 primary efficacy variables (see Table 11). The treatment effect of CIALIS did not diminish over time.

Table 11: Mean Endpoint and Change from Baseline for the Primary Efficacy Variables in the Two Primary US Trials
 | Study A |  |  | Study B
 | Placebo | CIALIS 20 mg |  | Placebo | CIALIS 20 mg
 | (N=49) | (N=146) | p-value | (N=48) | (N=159) | p-value
EF Domain Score
Endpoint | 13.5 | 19.5 |  | 13.6 | 22.5
Change from baseline | -0.2 | 6.9 | <.001 | 0.3 | 9.3 | <.001
Insertion of Penis (SEP2)
Endpoint | 39% | 62% |  | 43% | 77%
Change from baseline | 2% | 26% | <.001 | 2% | 32% | <.001
Maintenance of Erection (SEP3)
Endpoint | 25% | 50% |  | 23% | 64%
Change from baseline | 5% | 34% | <.001 | 4% | 44% | <.001

Results in General ED Population in Trials Outside the US — The 5 primary efficacy and safety studies conducted in the general ED population outside the US included 1112 patients, with a mean age of 59 years (range 21 to 82 years). The population was 76% White, 1% Black, 3% Hispanic, and 20% of other ethnicities, and included patients with ED of various severities, etiologies (organic, psychogenic, mixed), and with multiple co-morbid conditions, including diabetes mellitus, hypertension, and other cardiovascular disease. Most (90%) patients reported ED of at least 1-year duration. In these 5 trials, CIALIS 5, 10, and 20 mg showed clinically meaningful and statistically significant improvements in all 3 primary efficacy variables (see Tables 12, 13 and 14). The treatment effect of CIALIS did not diminish over time.

Table 12: Mean Endpoint and Change from Baseline for the EF Domain of the IIEF in the General ED Population in Five Primary Trials Outside the US
 | Placebo | CIALIS 5 mg | CIALIS 10 mg | CIALIS 20 mg
Study C
Endpoint [Change from baseline] | 15.0 [0.7] | 17.9 [4.0] | 20.0 [5.6]
 |  | p=.006 | p<.001
Study D
Endpoint [Change from baseline] | 14.4 [1.1] | 17.5 [5.1] | 20.6 [6.0]
 |  | p=.002 | p<.001
Study E
Endpoint [Change from baseline] | 18.1 [2.6] |  | 22.6 [8.1] | 25.0 [8.0]
 |  |  | p<.001 | p<.001
Study Fa
Endpoint [Change from baseline] | 12.7 [-1.6] |  |  | 22.8 [6.8]
 |  |  |  | p<.001
Study G
Endpoint [Change from baseline] | 14.5 [-0.9] |  | 21.2 [6.6] | 23.3 [8.0]
 |  |  | p<.001 | p<.001
a Treatment duration in Study F was 6 months

Table 13: Mean Post-Baseline Success Rate and Change from Baseline for SEP Question 2 (“Were you able to insert your penis into the partner's vagina?”) in the General ED Population in Five Pivotal Trials Outside the US
 | Placebo | CIALIS 5 mg | CIALIS 10 mg | CIALIS 20 mg
Study C
Endpoint [Change from baseline] | 49% [6%] | 57% [15%] | 73% [29%]
 |  | p=.063 | p<.001
Study D
Endpoint [Change from baseline] | 46% [2%] | 56% [18%] | 68% [15%]
 |  | p=.008 | p<.001
Study E
Endpoint [Change from baseline] | 55% [10%] |  | 77% [35%] | 85% [35%]
 |  |  | p<.001 | p<.001
Study Fa
Endpoint [Change from baseline] | 42% [-8%] |  |  | 81% [27%]
 |  |  |  | p<.001
Study G
Endpoint [Change from baseline] | 45% [-6%] |  | 73% [21%] | 76% [21%]
 |  |  | p<.001 | p<.001
a Treatment duration in Study F was 6 months

Table 14: Mean Post-Baseline Success Rate and Change from Baseline for SEP Question 3 (“Did your erection last long enough for you to have successful intercourse?”) in the General ED Population in Five Pivotal Trials Outside the US
 | Placebo | CIALIS 5 mg | CIALIS 10 mg | CIALIS 20 mg
Study C
Endpoint [Change from baseline] | 26% [4%] | 38% [19%] | 58% [32%]
 |  | p=.040 | p<.001
Study D
Endpoint [Change from baseline] | 28% [4%] | 42% [24%] | 51% [26%]
 |  | p<.001 | p<.001
Study E
Endpoint [Change from baseline] | 43% [15%] |  | 70% [48%] | 78% [50%]
 |  |  | p<.001 | p<.001
Study Fa
Endpoint [Change from baseline] | 27% [1%] |  |  | 74% [40%]
 |  |  |  | p<.001
Study G
Endpoint [Change from baseline] | 32% [5%] |  | 57% [33%] | 62% [29%]
 |  |  | p<.001 | p<.001
a Treatment duration in Study F was 6 months

In addition, there were improvements in EF domain scores, success rates based upon SEP Questions 2 and 3, and patient-reported improvement in erections across patients with ED of all degrees of disease severity while taking CIALIS, compared to patients on placebo.

Therefore, in all 7 primary efficacy and safety studies, CIALIS showed statistically significant improvement in patients' ability to achieve an erection sufficient for vaginal penetration and to maintain the erection long enough for successful intercourse, as measured by the IIEF questionnaire and by SEP diaries.

Efficacy Results in ED Patients with Diabetes Mellitus — CIALIS was shown to be effective in treating ED in patients with diabetes mellitus. Patients with diabetes were included in all 7 primary efficacy studies in the general ED population (N=235) and in one study that specifically assessed CIALIS in ED patients with type 1 or type 2 diabetes (N=216). In this randomized, placebo-controlled, double-blinded, parallel-arm design prospective trial, CIALIS demonstrated clinically meaningful and statistically significant improvement in erectile function, as measured by the EF domain of the IIEF questionnaire and Questions 2 and 3 of the SEP diary (see Table 15).

Table 15: Mean Endpoint and Change from Baseline for the Primary Efficacy Variables in a Study in ED Patients with Diabetes
 | Placebo | CIALIS 10 mg | CIALIS 20 mg
 | (N=71) | (N=73) | (N=72) | p-value
EF Domain Score
Endpoint [Change from baseline] | 12.2 [0.1] | 19.3 [6.4] | 18.7 [7.3] | <.001
Insertion of Penis (SEP2)
Endpoint [Change from baseline] | 30% [-4%] | 57% [22%] | 54% [23%] | <.001
Maintenance of Erection (SEP3)
Endpoint [Change from baseline] | 20% [2%] | 48% [28%] | 42% [29%] | <.001

Efficacy Results in ED Patients following Radical Prostatectomy — CIALIS was shown to be effective in treating patients who developed ED following bilateral nerve-sparing radical prostatectomy. In 1 randomized, placebo-controlled, double-blinded, parallel-arm design prospective trial in this population (N=303), CIALIS demonstrated clinically meaningful and statistically significant improvement in erectile function, as measured by the EF domain of the IIEF questionnaire and Questions 2 and 3 of the SEP diary (see Table 16).

Table 16: Mean Endpoint and Change from Baseline for the Primary Efficacy Variables in a Study in Patients who Developed ED Following Bilateral Nerve-Sparing Radical Prostatectomy
 | Placebo | CIALIS 20 mg
 | (N=102) | (N=201) | p-value
EF Domain Score
Endpoint [Change from baseline] | 13.3 [1.1] | 17.7 [5.3] | <.001
Insertion of Penis (SEP2)
Endpoint [Change from baseline] | 32% [2%] | 54% [22%] | <.001
Maintenance of Erection (SEP3)
Endpoint [Change from baseline] | 19% [4%] | 41% [23%] | <.001

Results in Studies to Determine the Optimal Use of CIALIS — Several studies were conducted with the objective of determining the optimal use of CIALIS in the treatment of ED. In one of these studies, the percentage of patients reporting successful erections within 30 minutes of dosing was determined. In this randomized, placebo-controlled, double-blinded trial, 223 patients were randomized to placebo, CIALIS 10, or 20 mg. Using a stopwatch, patients recorded the time following dosing at which a successful erection was obtained. A successful erection was defined as at least 1 erection in 4 attempts that led to successful intercourse. At or prior to 30 minutes, 35% (26/74), 38% (28/74), and 52% (39/75) of patients in the placebo, 10-, and 20-mg groups, respectively, reported successful erections as defined above.

Two studies were conducted to assess the efficacy of CIALIS at a given timepoint after dosing, specifically at 24 hours and at 36 hours after dosing.

In the first of these studies, 348 patients with ED were randomized to placebo or CIALIS 20 mg. Patients were encouraged to make 4 total attempts at intercourse; 2 attempts were to occur at 24 hours after dosing and 2 completely separate attempts were to occur at 36 hours after dosing. The results demonstrated a difference between the placebo group and the CIALIS group at each of the pre-specified timepoints. At the 24-hour timepoint, (more specifically, 22 to 26 hours), 53/144 (37%) patients reported at least 1 successful intercourse in the placebo group versus 84/138 (61%) in the CIALIS 20-mg group. At the 36-hour timepoint (more specifically, 33 to 39 hours), 49/133 (37%) of patients reported at least 1 successful intercourse in the placebo group versus 88/137 (64%) in the CIALIS 20-mg group.

In the second of these studies, a total of 483 patients were evenly randomized to 1 of 6 groups: 3 different dosing groups (placebo, CIALIS 10, or 20 mg) that were instructed to attempt intercourse at 2 different times (24 and 36 hours post-dosing). Patients were encouraged to make 4 separate attempts at their assigned dose and assigned timepoint. In this study, the results demonstrated a statistically significant difference between the placebo group and the CIALIS groups at each of the pre-specified timepoints. At the 24-hour timepoint, the mean, per patient percentage of attempts resulting in successful intercourse were 42, 56, and 67% for the placebo, CIALIS 10-, and 20-mg groups, respectively. At the 36-hour timepoint, the mean, per-patient percentage of attempts resulting in successful intercourse were 33, 56, and 62% for placebo, CIALIS 10-, and 20-mg groups, respectively.

14.2 CIALIS for Once Daily Use for ED

The efficacy and safety of CIALIS for once daily use in the treatment of erectile dysfunction has been evaluated in 2 clinical trials of 12-weeks duration and 1 clinical trial of 24-weeks duration, involving a total of 853 patients. CIALIS, when taken once daily, was shown to be effective in improving erectile function in men with erectile dysfunction (ED).

CIALIS was studied in the general ED population in 2 randomized, multicenter, double-blinded, placebo-controlled, parallel-arm design, primary efficacy and safety studies of 12- and 24-weeks duration, respectively. One of these studies was conducted in the United States and one was conducted in centers outside the US. An additional efficacy and safety study was performed in ED patients with diabetes mellitus. CIALIS was taken once daily at doses ranging from 2.5 to 10 mg. Food and alcohol intake were not restricted. Timing of sexual activity was not restricted relative to when patients took Cialis.

Results in General ED Population — The primary US efficacy and safety trial included a total of 287 patients, with a mean age of 59 years (range 25 to 82 years). The population was 86% White, 6% Black, 6% Hispanic, and 2% of other ethnicities, and included patients with ED of various severities, etiologies (organic, psychogenic, mixed), and with multiple co-morbid conditions, including diabetes mellitus, hypertension, and other cardiovascular disease. Most (>96%) patients reported ED of at least 1-year duration.

The primary efficacy and safety study conducted outside the US included 268 patients, with a mean age of 56 years (range 21 to 78 years). The population was 86% White, 3% Black, 0.4% Hispanic, and 10% of other ethnicities, and included patients with ED of various severities, etiologies (organic, psychogenic, mixed), and with multiple co-morbid conditions, including diabetes mellitus, hypertension, and other cardiovascular disease. Ninety-three percent of patients reported ED of at least 1-year duration.

In each of these trials, conducted without regard to the timing of dose and sexual intercourse, CIALIS demonstrated clinically meaningful and statistically significant improvement in erectile function, as measured by the EF domain of the IIEF questionnaire and Questions 2 and 3 of the SEP diary (see Table 17). When taken as directed, CIALIS was effective at improving erectile function.

In the 6 month double-blind study, the treatment effect of CIALIS did not diminish over time.

Table 17: Mean Endpoint and Change from Baseline for the Primary Efficacy Variables in the Two CIALIS for Once Daily Use Studies
 | Study Ha |  |  |  | Study Ib
 | Placebo | CIALIS 2.5 mg | CIALIS 5 mg |  | Placebo | CIALIS 5 mg
 | (N=94) | (N=96) | (N=97) | p-value | (N=54) | (N=109) | p-value
EF Domain Score
Endpoint | 14.6 | 19.1 | 20.8 |  | 15.0 | 22.8
Change from baseline | 1.2 | 6.1c | 7.0c | <.001 | 0.9 | 9.7c | <.001
Insertion of Penis (SEP2)
Endpoint | 51% | 65% | 71% |  | 52% | 79%
Change from baseline | 5% | 24%c | 26%c | <.001 | 11% | 37%c | <.001
Maintenance of Erection (SEP3)
Endpoint | 31% | 50% | 57% |  | 37% | 67%
Change from baseline | 10% | 31%c | 35%c | <.001 | 13% | 46%c | <.001
a Twenty-four-week study conducted in the US.
b Twelve-week study conducted outside the US.
c Statistically significantly different from placebo.

Efficacy Results in ED Patients with Diabetes Mellitus — CIALIS for once daily use was shown to be effective in treating ED in patients with diabetes mellitus. Patients with diabetes were included in both studies in the general ED population (N=79). A third randomized, multicenter, double-blinded, placebo-controlled, parallel-arm design trial included only ED patients with type 1 or type 2 diabetes (N=298). In this third trial, CIALIS demonstrated clinically meaningful and statistically significant improvement in erectile function, as measured by the EF domain of the IIEF questionnaire and Questions 2 and 3 of the SEP diary (see Table 18).

Table 18: Mean Endpoint and Change from Baseline for the Primary Efficacy Variables in a CIALIS for Once Daily Use Study in ED Patients with Diabetes
 | Placebo | CIALIS 2.5 mg | CIALIS 5 mg
 | (N=100) | (N=100) | (N=98) | p-value
EF Domain Score
Endpoint | 14.7 | 18.3 | 17.2
Change from baseline | 1.3 | 4.8a | 4.5a | <.001
Insertion of Penis (SEP2)
Endpoint | 43% | 62% | 61%
Change from baseline | 5% | 21%a | 29%a | <.001
Maintenance of Erection (SEP3)
Endpoint | 28% | 46% | 41%
Change from baseline | 8% | 26%a | 25%a | <.001
a Statistically significantly different from placebo.

14.3 CIALIS 5 mg for Once Daily Use for Benign Prostatic Hyperplasia (BPH)

The efficacy and safety of CIALIS for once daily use for the treatment of the signs and symptoms of BPH was evaluated in 3 randomized, multinational, double-blinded, placebo-controlled, parallel-design, efficacy and safety studies of 12 weeks duration. Two of these studies were in men with BPH and one study was specific to men with both ED and BPH [see Clinical Studies (14.4)]. The first study (Study J) randomized 1058 patients to receive either CIALIS 2.5 mg, 5 mg, 10 mg or 20 mg for once daily use or placebo. The second study (Study K) randomized 325 patients to receive either CIALIS 5 mg for once daily use or placebo. The full study population was 87% White, 2% Black, 11% other races; 15% was of Hispanic ethnicity. Patients with multiple co-morbid conditions such as diabetes mellitus, hypertension, and other cardiovascular disease were included.

The primary efficacy endpoint in the two studies that evaluated the effect of CIALIS for the signs and symptoms of BPH was the International Prostate Symptom Score (IPSS), a four week recall questionnaire that was administered at the beginning and end of a placebo run-in period and subsequently at follow-up visits after randomization. The IPSS assesses the severity of irritative (frequency, urgency, nocturia) and obstructive symptoms (incomplete emptying, stopping and starting, weak stream, and pushing or straining), with scores ranging from 0 to 35; higher numeric scores representing greater severity. Maximum urinary flow rate (Qmax), an objective measure of urine flow, was assessed as a secondary efficacy endpoint in Study J and as a safety endpoint in Study K.

The results for BPH patients with moderate to severe symptoms and a mean age of 63.2 years (range 44 to 87) who received either CIALIS 5 mg for once daily use or placebo (N=748) in Studies J and K are shown in Table 19 and Figures 5 and 6, respectively.

In each of these 2 trials, CIALIS 5 mg for once daily use resulted in statistically significant improvement in the total IPSS compared to placebo. Mean total IPSS showed a decrease starting at the first scheduled observation (4 weeks) in Study K and remained decreased through 12 weeks.

Table 19: Mean IPSS Changes in BPH Patients in Two CIALIS for Once Daily Use Studies
 | Study J |  |  | Study K
 | Placebo | CIALIS 5 mg |  | Placebo | CIALIS 5 mg
 | (N=205) | (N=205) | p-value | (N=164) | (N=160) | p-value
Total Symptom Score (IPSS)
Baseline | 17.1 | 17.3 |  | 16.6 | 17.1
Change from Baseline to Week 12 | -2.2 | -4.8 | <.001 | -3.6 | -5.6 | .004

Figure 5: Mean IPSS Changes in BPH Patients by Visit in Study J
Figure 6: Mean IPSS Changes in BPH Patients by Visit in Study K

In Study J, the effect of CIALIS 5 mg once daily on maximum urinary flow rate (Qmax) was evaluated as a secondary efficacy endpoint. Mean Qmax increased from baseline in both the treatment and placebo groups (CIALIS 5 mg: 1.6 mL/sec, placebo: 1.2 mL/sec); however, these changes were not significantly different between groups.

In Study K, the effect of CIALIS 5 mg once daily on Qmax was evaluated as a safety endpoint. Mean Qmax increased from baseline in both the treatment and placebo groups (CIALIS 5 mg: 1.6 mL/sec, placebo: 1.1 mL/sec); however, these changes were not significantly different between groups.

Efficacy Results in Patients with BPH initiating CIALIS and Finasteride – CIALIS for once daily use initiated together with finasteride was shown to be effective in treating the signs and symptoms of BPH in men with an enlarged prostate (>30 cc) for up to 26 weeks. This additional double-blinded, parallel-design study of 26 weeks duration randomized 696 men to initiate either CIALIS 5 mg with finasteride 5 mg or placebo with finasteride 5 mg. The study population had a mean age of 64 years (range 46-86). Patients with multiple co-morbid conditions such as erectile dysfunction, diabetes mellitus, hypertension, and other cardiovascular disease were included.

CIALIS with finasteride demonstrated statistically significant improvement in the signs and symptoms of BPH compared to placebo with finasteride, as measured by the total IPSS at 12 weeks, the primary study endpoint (see Table 20). Key secondary endpoints demonstrated improvement in total IPSS starting at the first scheduled observation at week 4 (CIALIS -4.0, placebo -2.3: p<.001) and the score remained decreased through 26 weeks (CIALIS -5.5, placebo -4.5; p=.022). However, the magnitude of the treatment difference between placebo/finasteride and CIALIS/finasteride decreased from 1.7 points at Week 4 to 1.0 point at Week 26, as shown in Table 20 and in Figure 7. The incremental benefit of CIALIS beyond 26 weeks is unknown.

Table 20: Mean Total IPSS Changes in BPH Patients in a CIALIS for Once Daily Use Study Together with Finasteride
 |  | Placebo and finasteride 5 mg |  | CIALIS 5mg and finasteride 5 mg | Treatment difference
 | n | (N=350)a | n | (N=345)a |  | p-valueb
Total Symptom Score (IPSS)
Baselinec | 349 | 17.4 | 344 | 17.1
Change from Baseline to Week 4b | 340 | -2.3 | 330 | -4.0 | -1.7 | <.001
Change from Baseline to Week 12b | 318 | -3.8 | 317 | -5.2 | -1.4 | .001
Change from Baseline to Week 26b | 295 | -4.5 | 308 | -5.5 | -1.0 | .022
a Overall ITT population.
b Mixed model for repeated measurements.
c Unadjusted mean.

Figure 7: Mean Total IPSS Changes By Visit in BPH Patients Taking CIALIS for Once Daily Use Together With Finasteride

In the 404 patients who had both ED and BPH at baseline, changes in erectile function were assessed as key secondary endpoints using the EF domain of the IIEF questionnaire. CIALIS with finasteride (N=203) was compared to placebo with finasteride (N=201). A statistically significant improvement from baseline (CIALIS/finasteride 13.7, placebo/finasteride 15.1) was observed at week 4 (CIALIS/finasteride 3.7, placebo/finasteride -1.1; p<.001), week 12 (CIALIS/finasteride 4.7, placebo/finasteride 0.6; p<.001), and week 26 (CIALIS/finasteride 4.7, placebo/finasteride 0.0; p<.001).

14.4 CIALIS 5 mg for Once Daily Use for ED and BPH

The efficacy and safety of CIALIS for once daily use for the treatment of ED, and the signs and symptoms of BPH, in patients with both conditions was evaluated in one placebo-controlled, multinational, double-blind, parallel-arm study which randomized 606 patients to receive either CIALIS 2.5 mg, 5 mg, for once daily use or placebo. ED severity ranged from mild to severe and BPH severity ranged from moderate to severe. The full study population had a mean age of 63 years (range 45 to 83) and was 93% White, 4% Black, 3% other races; 16% were of Hispanic ethnicity. Patients with multiple co-morbid conditions such as diabetes mellitus, hypertension, and other cardiovascular disease were included.

In this study, the co-primary endpoints were total IPSS and the Erectile Function (EF) domain score of the International Index of Erectile Function (IIEF). One of the key secondary endpoints in this study was Question 3 of the Sexual Encounter Profile diary (SEP3). Timing of sexual activity was not restricted relative to when patients took CIALIS.

The efficacy results for patients with both ED and BPH, who received either CIALIS 5 mg for once daily use or placebo (N=408) are shown in Tables 21 and 22 and Figure 8.

CIALIS 5 mg for once daily use resulted in statistically significant improvements in the total IPSS and in the EF domain of the IIEF questionnaire. CIALIS 5 mg for once daily use also resulted in statistically significant improvement in SEP3. CIALIS 2.5 mg did not result in statistically significant improvement in the total IPSS.

Table 21: Mean IPSS and IIEF EF Domain Changes in the CIALIS 5 mg for Once Daily Use Study in Patients with ED and BPH
 | Placebo | CIALIS 5 mg | p-value
Total Symptom Score (IPSS)
 | (N=193) | (N=206)
Baseline | 18.2 | 18.5
Change from Baseline to Week 12 | -3.8 | -6.1 | <.001
EF Domain Score (IIEF EF)
 | (N=188) | (N=202)
Baseline | 15.6 | 16.5
Endpoint | 17.6 | 22.9
Change from Baseline to Week 12 | 1.9 | 6.5 | <.001

Table 22: Mean SEP Question 3 Changes in the CIALIS 5 mg for Once Daily Use Study in Patients with ED and BPH
 | Placebo | CIALIS 5 mg
 | (N=187) | (N=199) | p-value
Maintenance of Erection (SEP3)
Baseline | 36% | 43%
Endpoint | 48% | 72%
Change from Baseline to Week 12 | 12% | 32% | <.001

CIALIS for once daily use resulted in improvement in the IPSS total score at the first scheduled observation (week 2) and throughout the 12 weeks of treatment (see Figure 8).

Figure 8: Mean IPSS Changes in ED/BPH Patients by Visit in Study L

In this study, the effect of CIALIS 5 mg once daily on Qmax was evaluated as a safety endpoint. Mean Qmax increased from baseline in both the treatment and placebo groups (CIALIS 5 mg: 1.6 mL/sec, placebo: 1.2 mL/sec); however, these changes were not significantly different between groups.

16 HOW SUPPLIED/STORAGE AND HANDLING

16.1 How Supplied

CIALIS (tadalafil) is supplied as follows:

Four strengths of almond-shaped tablets are available in different sizes and different shades of yellow, and supplied in the following package sizes:

2.5 mg tablets debossed with “C 2 1/2”

Blisters of 2 x 15

NDC 0002-4465-34

5 mg tablets debossed with “C 5”

Bottles of 30

NDC 0002-4462-30

10 mg tablets debossed with “C 10”

Bottles of 30

NDC 0002-4463-30

20 mg tablets debossed with “C 20”

Bottles of 30

NDC 0002-4464-30

16.2 Storage

Store at 25°C (77°F); excursions permitted to 15-30°C (59-86°F) [see USP Controlled Room Temperature].

Keep out of reach of children.

17 PATIENT COUNSELING INFORMATION

“See FDA-approved patient labeling (Patient Information)”

17.1 Nitrates

Physicians should discuss with patients the contraindication of CIALIS with regular and/or intermittent use of organic nitrates. Patients should be counseled that concomitant use of CIALIS with nitrates could cause blood pressure to suddenly drop to an unsafe level, resulting in dizziness, syncope, or even heart attack or stroke.

Physicians should discuss with patients the appropriate action in the event that they experience anginal chest pain requiring nitroglycerin following intake of CIALIS. In such a patient, who has taken CIALIS, where nitrate administration is deemed medically necessary for a life-threatening situation, at least 48 hours should have elapsed after the last dose of CIALIS before nitrate administration is considered. In such circumstances, nitrates should still only be administered under close medical supervision with appropriate hemodynamic monitoring. Therefore, patients who experience anginal chest pain after taking CIALIS should seek immediate medical attention [see Contraindications (4.1) and Warnings and Precautions (5.1)].

17.2 Guanylate Cyclase (GC) Stimulators

Physicians should discuss with patients the contraindication of CIALIS with any use of a GC stimulator, such as riociguat, for pulmonary arterial hypertension. Patients should be counseled that the concomitant use of CIALIS with GC stimulators may cause blood pressure to drop to an unsafe level.

17.3 Cardiovascular Considerations

Physicians should consider the potential cardiac risk of sexual activity in patients with preexisting cardiovascular disease. Physicians should advise patients who experience symptoms upon initiation of sexual activity to refrain from further sexual activity and seek immediate medical attention [see Warnings and Precautions (5.1)].

17.4 Concomitant Use with Drugs Which Lower Blood Pressure

Physicians should discuss with patients the potential for CIALIS to augment the blood-pressure-lowering effect of alpha-blockers, and antihypertensive medications [see Warnings and Precautions (5.6), Drug Interactions (7.1), and Clinical Pharmacology (12.2)].

17.5 Potential for Drug Interactions When Taking CIALIS for Once Daily Use

Physicians should discuss with patients the clinical implications of continuous exposure to tadalafil when prescribing CIALIS for once daily use, especially the potential for interactions with medications (e.g., nitrates, alpha-blockers, antihypertensives and potent inhibitors of cytochrome P450 3A4) and with substantial consumption of alcohol. [see Dosage and Administration (2.7), Warnings and Precautions (5.6), Drug Interactions (7.1, 7.2), Clinical Pharmacology (12.2), and Clinical Studies (14.2)].

17.6 Priapism

There have been rare reports of prolonged erections greater than 4 hours and priapism (painful erections greater than 6 hours in duration) for this class of compounds. Priapism, if not treated promptly, can result in irreversible damage to the erectile tissue. Physicians should advise patients who have an erection lasting greater than 4 hours, whether painful or not, to seek emergency medical attention.

17.7 Sudden Loss of Vision

Physicians should advise patients to stop use of all PDE5 inhibitors, including CIALIS, and seek medical attention in the event of a sudden loss of vision in one or both eyes. Such an event may be a sign of non-arteritic anterior ischemic optic neuropathy (NAION), a cause of decreased vision, including possible permanent loss of vision, that has been reported rarely postmarketing in temporal association with the use of all PDE5 inhibitors. Physicians should discuss with patients the increased risk of NAION in individuals who have already experienced NAION in one eye. Physicians should also discuss with patients the increased risk of NAION among the general population in patients with a "crowded" optic disc, although evidence is insufficient to support screening of prospective users of PDE5 inhibitors, including CIALIS, for this uncommon condition [see Warnings and Precautions (5.4) and Adverse Reactions (6.2)].

17.8 Sudden Hearing Loss

Physicians should advise patients to stop taking PDE5 inhibitors, including CIALIS, and seek prompt medical attention in the event of sudden decrease or loss of hearing. These events, which may be accompanied by tinnitus and dizziness, have been reported in temporal association to the intake of PDE5 inhibitors, including CIALIS. It is not possible to determine whether these events are related directly to the use of PDE5 inhibitors or to other factors [see Adverse Reactions (6.1, 6.2)].

17.9 Alcohol

Patients should be made aware that both alcohol and CIALIS, a PDE5 inhibitor, act as mild vasodilators. When mild vasodilators are taken in combination, blood-pressure-lowering effects of each individual compound may be increased. Therefore, physicians should inform patients that substantial consumption of alcohol (e.g., 5 units or greater) in combination with CIALIS can increase the potential for orthostatic signs and symptoms, including increase in heart rate, decrease in standing blood pressure, dizziness, and headache [see Warnings and Precautions (5.9), Drug Interactions (7.1), and Clinical Pharmacology (12.2)].

17.10 Sexually Transmitted Disease

The use of CIALIS offers no protection against sexually transmitted diseases. Counseling of patients about the protective measures necessary to guard against sexually transmitted diseases, including Human Immunodeficiency Virus (HIV) should be considered.

17.11 Recommended Administration

Physicians should instruct patients on the appropriate administration of CIALIS to allow optimal use.

For CIALIS for use as needed in men with ED, patients should be instructed to take one tablet at least 30 minutes before anticipated sexual activity. In most patients, the ability to have sexual intercourse is improved for up to 36 hours.

For CIALIS for once daily use in men with ED or ED/BPH, patients should be instructed to take one tablet at approximately the same time every day without regard for the timing of sexual activity. Cialis is effective at improving erectile function over the course of therapy.

For CIALIS for once daily use in men with BPH, patients should be instructed to take one tablet at approximately the same time every day.

Revision Date: 04/2023

Marketed by: Lilly USA, LLC
Indianapolis, IN 46285, USA

www.cialis.com

Copyright © 2003, 2023, Eli Lilly and Company. All rights reserved.

CLS-0005-USPI-20230425

Patient Information

CIALIS® (See-AL-iss)

(tadalafil) tablets

Read this important information before you start taking CIALIS and each time you get a refill. There may be new information. You may also find it helpful to share this information with your partner. This information does not take the place of talking with your healthcare provider. You and your healthcare provider should talk about CIALIS when you start taking it and at regular checkups. If you do not understand the information, or have questions, talk with your healthcare provider or pharmacist.

What Is The Most Important Information I Should Know About CIALIS?

CIALIS can cause your blood pressure to drop suddenly to an unsafe level if it is taken with certain other medicines. You could get dizzy, faint, or have a heart attack or stroke. Never take CIALIS with any nitrate or guanylate cyclase stimulator medicines.

Do not take CIALIS if you take any medicines called “nitrates.” Nitrates are commonly used to treat angina. Angina is a symptom of heart disease and can cause pain in your chest, jaw, or down your arm.

- Medicines called nitrates include nitroglycerin that is found in tablets, sprays, ointments, pastes, or patches. Nitrates can also be found in other medicines such as isosorbide dinitrate or isosorbide mononitrate. Some recreational drugs called “poppers” also contain nitrates, such as amyl nitrite and butyl nitrite.

Do not take CIALIS if you take medicines called guanylate cyclase stimulators which include:

- Riociguat (Adempas®) a medicine that treats pulmonary arterial hypertension and chronic-thromboembolic pulmonary hypertension.

Ask your healthcare provider or pharmacist if you are not sure if any of your medicines are nitrates or guanylate cyclase stimulators, such as riociguat.

(See “Who Should Not Take CIALIS?”)

Tell all of your healthcare providers that you take CIALIS. If you need emergency medical care for a heart problem, it will be important for your healthcare provider to know when you last took CIALIS.

After taking a single tablet, some of the active ingredient of CIALIS remains in your body for more than 2 days. The active ingredient can remain longer if you have problems with your kidneys or liver, or you are taking certain other medications (see “Can Other Medicines Affect CIALIS?”).

Stop sexual activity and get medical help right away if you get symptoms such as chest pain, dizziness, or nausea during sex. Sexual activity can put an extra strain on your heart, especially if your heart is already weak from a heart attack or heart disease.

See also “What Are The Possible Side Effects Of CIALIS?”

What Is CIALIS?

CIALIS is a prescription medicine taken by mouth for the treatment of:

- men with erectile dysfunction (ED)
- men with symptoms of benign prostatic hyperplasia (BPH)
- men with both ED and BPH

CIALIS for the Treatment of ED

ED is a condition where the penis does not fill with enough blood to harden and expand when a man is sexually excited, or when he cannot keep an erection. A man who has trouble getting or keeping an erection should see his healthcare provider for help if the condition bothers him. CIALIS helps increase blood flow to the penis and may help men with ED get and keep an erection satisfactory for sexual activity. Once a man has completed sexual activity, blood flow to his penis decreases, and his erection goes away.

Some form of sexual stimulation is needed for an erection to happen with CIALIS.

CIALIS does not:

- cure ED
- increase a man's sexual desire
- protect a man or his partner from sexually transmitted diseases, including HIV. Speak to your healthcare provider about ways to guard against sexually transmitted diseases.
- serve as a male form of birth control

CIALIS is only for men over the age of 18, including men with diabetes or who have undergone prostatectomy.

CIALIS for the Treatment of Symptoms of BPH

BPH is a condition that happens in men, where the prostate gland enlarges which can cause urinary symptoms.

CIALIS for the Treatment of ED and Symptoms of BPH

ED and symptoms of BPH may happen in the same person and at the same time. Men who have both ED and symptoms of BPH may take CIALIS for the treatment of both conditions.

CIALIS is not for women or children.

CIALIS must be used only under a healthcare provider's care.

Who Should Not Take CIALIS?

Do not take CIALIS if you:

- take any medicines called “nitrates”.
- use recreational drugs called “poppers” like amyl nitrite and butyl nitrite. (See “What Is The Most Important Information I Should Know About CIALIS?”)
- take any medicines called guanylate cyclase stimulators, such as riociguat.
- are allergic to CIALIS or ADCIRCA®, or any of its ingredients. See the end of this leaflet for a complete list of ingredients in CIALIS. Symptoms of an allergic reaction may include:
  - rash
  - hives
  - swelling of the lips, tongue, or throat
  - difficulty breathing or swallowing

Call your healthcare provider or get help right away if you have any of the symptoms of an allergic reaction listed above.

What Should I Tell My Healthcare Provider Before Taking CIALIS?

CIALIS is not right for everyone. Only your healthcare provider and you can decide if CIALIS is right for you. Before taking CIALIS, tell your healthcare provider about all your medical problems, including if you:

- have heart problems such as angina, heart failure, irregular heartbeats, or have had a heart attack. Ask your healthcare provider if it is safe for you to have sexual activity. You should not take CIALIS if your healthcare provider has told you not to have sexual activity because of your health problems.
- have pulmonary hypertension
- have low blood pressure or have high blood pressure that is not controlled
- have had a stroke
- have liver problems
- have kidney problems or require dialysis
- have retinitis pigmentosa, a rare genetic (runs in families) eye disease
- have ever had severe vision loss, including a condition called NAION
- have stomach ulcers
- have a bleeding problem
- have a deformed penis shape or Peyronie's disease
- have had an erection that lasted more than 4 hours
- have blood cell problems such as sickle cell anemia, multiple myeloma, or leukemia

Can Other Medicines Affect CIALIS?

Tell your healthcare provider about all the medicines you take including prescription and non-prescription medicines, vitamins, and herbal supplements. CIALIS and other medicines may affect each other. Always check with your healthcare provider before starting or stopping any medicines. Especially tell your healthcare provider if you take any of the following*:

- medicines called nitrates (see “What Is The Most Important Information I Should Know About CIALIS?”)
- medicines called guanylate cyclase stimulators, such as riociguat (Adempas®), used to treat pulmonary hypertension
- medicines called alpha blockers. These include Hytrin® (terazosin HCl), Flomax® (tamsulosin HCl), Cardura® (doxazosin mesylate), Minipress® (prazosin HCl), Uroxatral® (alfuzosin HCl), Jalyn® (dutasteride and tamsulosin HCl) or Rapaflo® (silodosin). Alpha-blockers are sometimes prescribed for prostate problems or high blood pressure. If CIALIS is taken with certain alpha blockers, your blood pressure could suddenly drop. You could get dizzy or faint.
- other medicines to treat high blood pressure (hypertension)
- medicines called HIV protease inhibitors, such as ritonavir (Norvir®, Kaletra®)
- some types of oral antifungals such as ketoconazole (Nizoral®), itraconazole (Sporanox®)
- some types of antibiotics such as clarithromycin (Biaxin®), telithromycin (Ketek®), erythromycin (several brand names exist. Please consult your healthcare provider to determine if you are taking this medicine).
- other medicines or treatments for ED.
- CIALIS is also marketed as ADCIRCA for the treatment of pulmonary arterial hypertension. Do not take both CIALIS and ADCIRCA. Do not take sildenafil citrate (Revatio®) with CIALIS.

How Should I Take CIALIS?

- Take CIALIS exactly as your healthcare provider prescribes it. Your healthcare provider will prescribe the dose that is right for you.
- Some men can only take a low dose of CIALIS or may have to take it less often, because of medical conditions or medicines they take.
- Do not change your dose or the way you take CIALIS without talking to your healthcare provider. Your healthcare provider may lower or raise your dose, depending on how your body reacts to CIALIS and your health condition.
- CIALIS may be taken with or without meals.
- If you take too much CIALIS, call your healthcare provider or emergency room right away.

How Should I Take CIALIS for Symptoms of BPH?

For symptoms of BPH, CIALIS is taken once daily.

- Do not take CIALIS more than one time each day.
- Take one CIALIS tablet every day at about the same time of day.
- If you miss a dose, you may take it when you remember but do not take more than one dose per day.

How Should I Take CIALIS for ED?

For ED, there are two ways to take CIALIS - either for use as needed OR for use once daily.

CIALIS for use as needed:

- Do not take CIALIS more than one time each day.
- Take one CIALIS tablet before you expect to have sexual activity. You may be able to have sexual activity at 30 minutes after taking CIALIS and up to 36 hours after taking it. You and your healthcare provider should consider this in deciding when you should take CIALIS before sexual activity. Some form of sexual stimulation is needed for an erection to happen with CIALIS.
- Your healthcare provider may change your dose of CIALIS depending on how you respond to the medicine, and on your health condition.

OR

CIALIS for once daily use is a lower dose you take every day.

- Do not take CIALIS more than one time each day.
- Take one CIALIS tablet every day at about the same time of day. You may attempt sexual activity at any time between doses.
- If you miss a dose, you may take it when you remember but do not take more than one dose per day.
- Some form of sexual stimulation is needed for an erection to happen with CIALIS.
- Your healthcare provider may change your dose of CIALIS depending on how you respond to the medicine, and on your health condition.

How Should I Take CIALIS for Both ED and the Symptoms of BPH?

For both ED and the symptoms of BPH, CIALIS is taken once daily.

- Do not take CIALIS more than one time each day.
- Take one CIALIS tablet every day at about the same time of day. You may attempt sexual activity at any time between doses.
- If you miss a dose, you may take it when you remember but do not take more than one dose per day.
- Some form of sexual stimulation is needed for an erection to happen with CIALIS.

What Should I Avoid While Taking CIALIS?

- Do not use other ED medicines or ED treatments while taking CIALIS.
- Do not drink too much alcohol when taking CIALIS (for example, 5 glasses of wine or 5 shots of whiskey). Drinking too much alcohol can increase your chances of getting a headache or getting dizzy, increasing your heart rate, or lowering your blood pressure.

What Are The Possible Side Effects Of CIALIS?

See “What Is The Most Important Information I Should Know About CIALIS?”

The most common side effects with CIALIS are: headache, indigestion, back pain, muscle aches, flushing, and stuffy or runny nose. These side effects usually go away after a few hours. Men who get back pain and muscle aches usually get it 12 to 24 hours after taking CIALIS. Back pain and muscle aches usually go away within 2 days.

Call your healthcare provider if you get any side effect that bothers you or one that does not go away.

Uncommon side effects include:

An erection that won't go away (priapism). If you get an erection that lasts more than 4 hours, get medical help right away. Priapism must be treated as soon as possible or lasting damage can happen to your penis, including the inability to have erections.

Color vision changes, such as seeing a blue tinge (shade) to objects or having difficulty telling the difference between the colors blue and green.

In rare instances, men taking PDE5 inhibitors (oral erectile dysfunction medicines, including CIALIS) reported a sudden decrease or loss of vision in one or both eyes. It is uncertain whether PDE5 inhibitors directly cause the vision loss. If you experience sudden decrease or loss of vision, stop taking PDE5 inhibitors, including CIALIS, and call a healthcare provider right away.

Sudden loss or decrease in hearing, sometimes with ringing in the ears and dizziness, has been rarely reported in people taking PDE5 inhibitors, including CIALIS. It is not possible to determine whether these events are related directly to the PDE5 inhibitors, to other diseases or medications, to other factors, or to a combination of factors. If you experience these symptoms, stop taking CIALIS and contact a healthcare provider right away.

These are not all the possible side effects of CIALIS. For more information, ask your healthcare provider or pharmacist.

How Should I Store CIALIS?

Store CIALIS at room temperature between 59° and 86°F (15° and 30°C).

Keep CIALIS and all medicines out of the reach of children.

General Information About CIALIS:

Medicines are sometimes prescribed for conditions other than those described in patient information leaflets. Do not use CIALIS for a condition for which it was not prescribed. Do not give CIALIS to other people, even if they have the same symptoms that you have. It may harm them.

This is a summary of the most important information about CIALIS. If you would like more information, talk with your healthcare provider. You can ask your healthcare provider or pharmacist for information about CIALIS that is written for health providers. For more information you can also visit www.cialis.com, or call 1-877-CIALIS1 (1-877-242-5471).

What Are The Ingredients In CIALIS?

Active Ingredient: tadalafil

Inactive Ingredients: croscarmellose sodium, hydroxypropyl cellulose, hypromellose, iron oxide, lactose monohydrate, magnesium stearate, microcrystalline cellulose, sodium lauryl sulfate, talc, titanium dioxide, and triacetin.

This Patient Information has been approved by the U.S. Food and Drug Administration

Rx only

CIALIS® (tadalafil) is a registered trademark of Eli Lilly and Company.

*The brands listed are trademarks of their respective owners and are not trademarks of Eli Lilly and Company. The makers of these brands are not affiliated with and do not endorse Eli Lilly and Company or its products.

Revision Date: 05/2017

Marketed by: Lilly USA, LLC
Indianapolis, IN 46285, USA

www.cialis.com

Copyright © 2003, 2017, Eli Lilly and Company. All rights reserved.

CLS-0002-PPI-20170505

PACKAGE LABEL

PACKAGE LABEL – Cialis 2.5 mg tablets, 30 count, blister pack

30 tablets (2 cards of 15 tablets)

Each tablet contains 2.5 mg of tadalafil.

NDC 0002-4465-34

TA 4465

Cialis®

(tadalafil) tablets

2.5 mg

for once daily use

Rx only

www.cialis.com

Lilly

PACKAGE LABEL – Cialis 5mg tablets, 30 count, bottle

NDC 0002-4462-30

30 Tablets

Cialis®

(tadalafil) tablets

5mg

Tablets should not be split.

Entire dose should be taken.

Rx only

Lilly

PACKAGE LABEL – Cialis 10mg tablets, 30 count, bottle

NDC 0002-4463-30

30 Tablets

Cialis®

(tadalafil) tablets

10mg

Tablets should not be split.

Entire dose should be taken.

Rx only

Lilly

PACKAGE LABEL

PACKAGE LABEL – Cialis 20 mg tablets, 30 count, bottle

NDC 0002-4464-30

30 Tablets

Cialis®

(tadalafil) tablets

20mg

Tablets should not be split.

Entire dose should be taken.

Rx only

Lilly